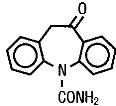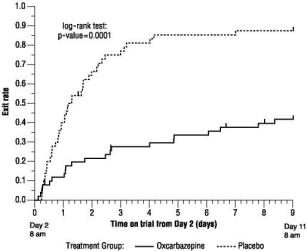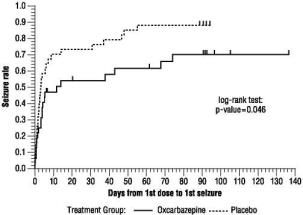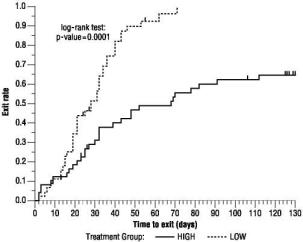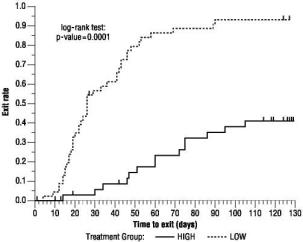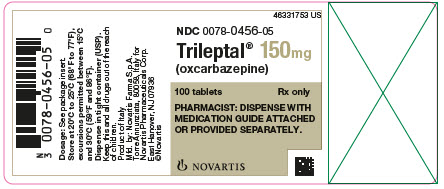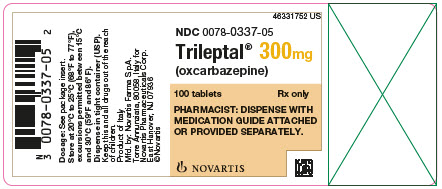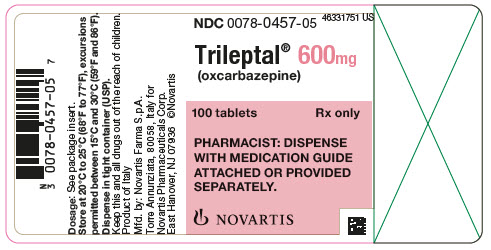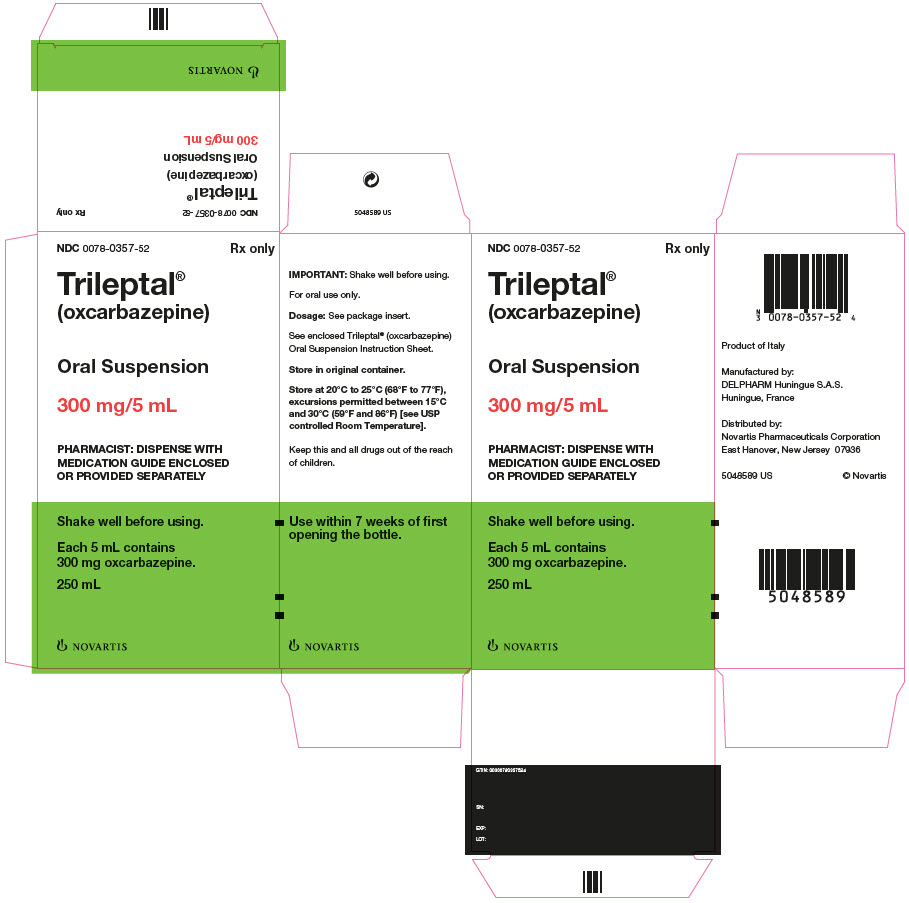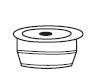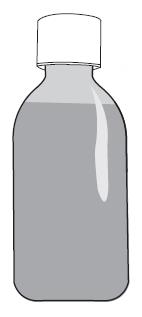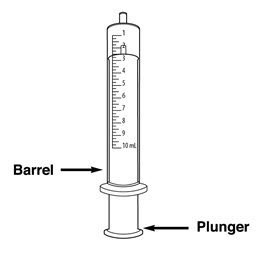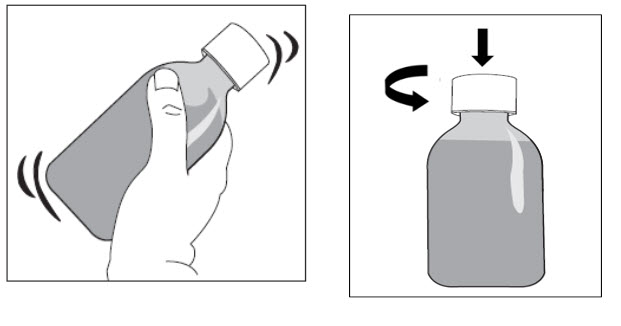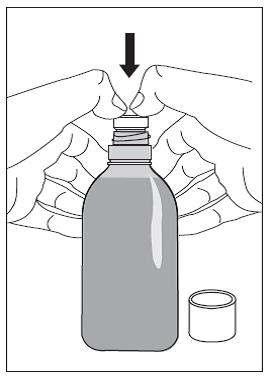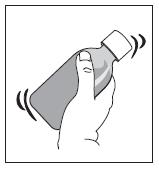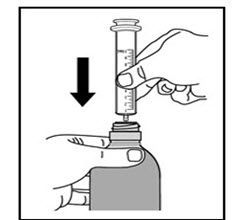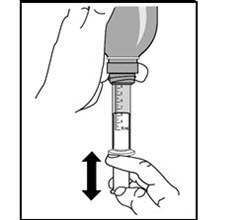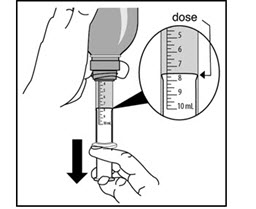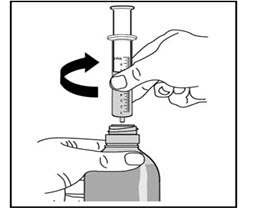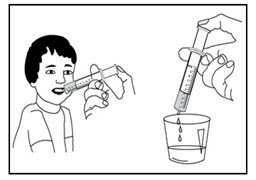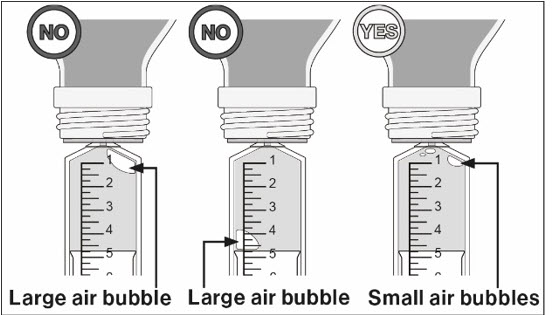 DRUG LABEL: Trileptal
NDC: 0078-0456 | Form: TABLET, FILM COATED
Manufacturer: Novartis Pharmaceuticals Corporation
Category: prescription | Type: HUMAN PRESCRIPTION DRUG LABEL
Date: 20251216

ACTIVE INGREDIENTS: OXCARBAZEPINE 150 mg/1 1
INACTIVE INGREDIENTS: CELLULOSE, MICROCRYSTALLINE; CROSPOVIDONE; HYPROMELLOSES; MAGNESIUM STEARATE; TITANIUM DIOXIDE; SILICON DIOXIDE; TALC; POLYETHYLENE GLYCOL; FERRIC OXIDE YELLOW; WATER

HIGHLIGHTS OF PRESCRIBING INFORMATION

These highlights do not include all the information needed to use TRILEPTAL safely and effectively. See full prescribing information for TRILEPTAL.
TRILEPTAL® (oxcarbazepine) film-coated tablets, for oral use
TRILEPTAL® (oxcarbazepine) oral suspension
Initial U.S. Approval: 2000

RECENT MAJOR CHANGES

Dosage and Administration (2.8) | 9/2025

1 INDICATIONS AND USAGE

TRILEPTAL is indicated for:

- Adults: Monotherapy or adjunctive therapy in the treatment of partial-onset seizures
- Pediatrics:
  - Monotherapy in the treatment of partial-onset seizures in children 4-16 years
  - Adjunctive therapy in the treatment of partial-onset seizures in children 2-16 years (1)

2 DOSAGE AND ADMINISTRATION

Adults: Initiate with a dose of 600 mg/day, given twice a day

- Adjunctive Therapy: Maximum increment of 600 mg/day at approximately weekly intervals. The recommended daily dose is 1200 mg/day (2.1)
- Conversion to Monotherapy: Withdrawal concomitant over 3 to 6 weeks; reach maximum dose of TRILEPTAL in 2 to 4 weeks with increments of 600 mg/day at weekly intervals to a recommended daily dose of 2400 mg/day (2.2)
- Initiation of Monotherapy: Increments of 300 mg/day every third day to a dose of 1200 mg/day (2.3)
- Initiate at one-half the usual starting dose and increase slowly in patients with a creatinine clearance < 30 mL/min (2.7)

Pediatrics: Initiation with 8 to 10 mg/kg/day, given twice a day. For patients aged 2 to < 4 years and under 20 kg, a starting dose of 16 to 20 mg/kg/day may be considered. Recommended daily dose is dependent upon patient weight.

- Adjunctive Patients (Aged 2-16 Years): For patients aged 4 to 16 years, target maintenance dose should be achieved over 2 weeks (2.4). For patients aged 2 to < 4 years, maximum maintenance dose should be achieved over 2 to 4 weeks and should not exceed 60 mg/kg/day (2.4)
- Conversion to Monotherapy for Patients (Aged 4-16 Years): Maximum increment of 10 mg/kg/day at weekly intervals, concomitant antiepileptic drugs (AEDs) can be completely withdrawn over 3 to 6 weeks (2.5)
- Initiation of Monotherapy for Patients (Aged 4-16 Years): Increments of 5 mg/kg/day every third day (2.6)

3 DOSAGE FORMS AND STRENGTHS

- Film-coated tablets: 150 mg, 300 mg and 600 mg (3)
- Oral suspension: 300 mg/5 mL (60 mg/mL) (3)

4 CONTRAINDICATIONS

Known hypersensitivity to oxcarbazepine or to any of its components, or to eslicarbazepine acetate (4, 5.2)

5 WARNINGS AND PRECAUTIONS

- Hyponatremia: Monitor serum sodium levels (5.1)
- Cross Hypersensitivity Reaction to Carbamazepine: Discontinue immediately if hypersensitivity occurs (5.3)
- Serious Dermatological Reactions: If occurs, consider discontinuation (5.4)
- Suicidal Behavior and Ideation: Monitor for suicidal thoughts/behavior (5.5)
- Withdrawal of AEDs: Withdraw TRILEPTAL gradually (5.6)
- Cognitive/Neuropsychiatric Adverse Reactions: May cause cognitive dysfunction, somnolence, and coordination abnormalities. Use caution when operating machinery (5.7)
- Drug Reaction with Eosinophilia and Systemic Symptoms (DRESS)/Multi-Organ Hypersensitivity: Monitor and discontinue if another cause cannot be established (5.8)
- Hematologic Events: Consider discontinuing (5.9)
- Seizure Control During Pregnancy: Active metabolite may decrease (5.10)
- Risk of Seizure Aggravation: Discontinue if occurs (5.11)

6 ADVERSE REACTIONS

The most common (≥ 10% more than placebo for adjunctive or low dose for monotherapy) adverse reactions in adults and pediatrics were: dizziness, somnolence, diplopia, fatigue, nausea, vomiting, ataxia, abnormal vision, headache, nystagmus, tremor, and abnormal gait (6.1)

To report SUSPECTED ADVERSE REACTIONS, contact Novartis Pharmaceuticals Corporation at 1-888-669-6682 or FDA at 1-800-FDA-1088 or www.fda.gov/medwatch.

7 DRUG INTERACTIONS

- Phenytoin: Increased phenytoin levels. Reduced dose of phenytoin may be required (7.1)
- Carbamazepine, Phenytoin, and Phenobarbital: Decreased plasma levels of MHD (the active metabolite). Dose adjustments may be necessary (7.1)
- Oral Contraceptive: TRILEPTAL may decrease the effectiveness of hormonal contraceptives (7.3)

8 USE IN SPECIFIC POPULATIONS

- Pregnancy: May cause fetal harm (8.1)

FULL PRESCRIBING INFORMATION

1 INDICATIONS AND USAGE

TRILEPTAL is indicated for use as monotherapy or adjunctive therapy in the treatment of partial-onset seizures in adults and as monotherapy in the treatment of partial-onset seizures in pediatric patients aged 4 years and above, and as adjunctive therapy in pediatric patients aged 2 years and above with partial-onset seizures.

2 DOSAGE AND ADMINISTRATION

2.1 Adjunctive Therapy for Adults

Initiate TRILEPTAL with a dose of 600 mg/day, given twice a day. If clinically indicated, the dose may be increased by a maximum of 600 mg/day at approximately weekly intervals; the maximum recommended daily dose is 1200 mg/day. Daily doses above 1200 mg/day show somewhat greater effectiveness in controlled trials, but most patients were not able to tolerate the 2400 mg/day dose, primarily because of central nervous (CNS) effects.

Dosage adjustment is recommended with concomitant use of strong CYP3A4 enzyme inducers or UDP-glucuronosyltransferases (UGT) inducers, which include certain antiepileptic drugs (AEDs) [see Drug Interactions (7.1, 7.2)].

2.2 Conversion to Monotherapy for Adults

Patients receiving concomitant AEDs may be converted to monotherapy by initiating treatment with TRILEPTAL at 600 mg/day (given in a twice a day regimen) while simultaneously initiating the reduction of the dose of the concomitant AEDs. The concomitant AEDs should be completely withdrawn over 3 to 6 weeks, while the maximum dose of TRILEPTAL should be reached in about 2 to 4 weeks. TRILEPTAL may be increased as clinically indicated by a maximum increment of 600 mg/day at approximately weekly intervals to achieve the maximum recommended daily dose of 2400 mg/day. A daily dose of 1200 mg/day has been shown in one study to be effective in patients in whom monotherapy has been initiated with TRILEPTAL. Patients should be observed closely during this transition phase.

2.3 Initiation of Monotherapy for Adults

Patients not currently being treated with AEDs may have monotherapy initiated with TRILEPTAL. In these patients, initiate TRILEPTAL at a dose of 600 mg/day (given twice a day); the dose should be increased by 300 mg/day every third day to a dose of 1200 mg/day. Controlled trials in these patients examined the effectiveness of a 1200 mg/day dose; a dose of 2400 mg/day has been shown to be effective in patients converted from other AEDs to TRILEPTAL monotherapy (see above).

2.4 Adjunctive Therapy for Pediatric Patients (Aged 2-16 Years)

In pediatric patients aged 4-16 years, initiate TRILEPTAL at a daily dose of 8 to 10 mg/kg generally not to exceed 600 mg/day, given twice a day. The target maintenance dose of TRILEPTAL should be achieved over 2 weeks, and is dependent upon patient weight, according to the following chart:

- 20 to 29 kg-900 mg/day
- 29.1 to 39 kg-1200 mg/day
- 39 kg-1800 mg/day

In the clinical trial, in which the intention was to reach these target doses, the median daily dose was 31 mg/kg with a range of 6 to 51 mg/kg.

In pediatric patients aged 2 to < 4 years, initiate TRILEPTAL at a daily dose of 8 to 10 mg/kg generally not to exceed 600 mg/day, given twice a day. For patients less than 20 kg, a starting dose of 16 to 20 mg/kg may be considered [see Clinical Pharmacology (12.3)]. The maximum maintenance dose of TRILEPTAL should be achieved over 2 to 4 weeks and should not exceed 60 mg/kg/day in a twice a day regimen.

In the clinical trial in pediatric patients (2 to 4 years of age), in which the intention was to reach the target dose of 60 mg/kg/day, 50% of patients reached a final dose of at least 55 mg/kg/day.

Under adjunctive therapy (with and without enzyme-inducing AEDs), when normalized by body weight, apparent clearance (L/hr/kg) decreased when age increased such that children 2 to < 4 years of age may require up to twice the oxcarbazepine dose per body weight compared to adults; and children 4 to ≤ 12 years of age may require a 50% higher oxcarbazepine dose per body weight compared to adults.

Dosage adjustment is recommended with concomitant use of strong CYP3A4 enzyme inducers or UGT inducers, which include certain AEDs [see Drug Interactions (7.1, 7.2)].

2.5 Conversion to Monotherapy for Pediatric Patients (Aged 4-16 Years)

Patients receiving concomitant AEDs may be converted to monotherapy by initiating treatment with TRILEPTAL at approximately 8 to 10 mg/kg/day given twice a day, while simultaneously initiating the reduction of the dose of the concomitant AEDs. The concomitant AEDs can be completely withdrawn over 3 to 6 weeks, while TRILEPTAL may be increased as clinically indicated by a maximum increment of 10 mg/kg/day at approximately weekly intervals to achieve the recommended daily dose. Patients should be observed closely during this transition phase.

The recommended total daily dose of TRILEPTAL is shown in Table 1.

2.6 Initiation of Monotherapy for Pediatric Patients (Aged 4-16 Years)

Patients not currently being treated with AEDs may have monotherapy initiated with TRILEPTAL. In these patients, initiate TRILEPTAL at a dose of 8 to 10 mg/kg/day given twice a day. The dose should be increased by 5 mg/kg/day every third day to the recommended daily dose shown in the table below.

Table 1: Range of Maintenance Doses of TRILEPTAL for Pediatrics by Weight During Monotherapy
Weight in kg | From | To
 | Dose (mg/day) | Dose (mg/day)
20 | 600 | 900
25 | 900 | 1200
30 | 900 | 1200
35 | 900 | 1500
40 | 900 | 1500
45 | 1200 | 1500
50 | 1200 | 1800
55 | 1200 | 1800
60 | 1200 | 2100
65 | 1200 | 2100
70 | 1500 | 2100

2.7 Dosage Modification for Patients With Renal Impairment

In patients with impaired renal function (creatinine clearance < 30 mL/min), initiate TRILEPTAL at one-half the usual starting dose (300 mg/day, given twice a day), and increase slowly to achieve the desired clinical response [see Clinical Pharmacology (12.3)].

2.8 Administration Information

TRILEPTAL can be taken with or without food [see Clinical Pharmacology (12.3)].

Before using TRILEPTAL oral suspension, shake the bottle well and prepare the dose immediately afterwards. The prescribed amount of oral suspension should be withdrawn from the bottle using the oral dosing syringe supplied. A household teaspoon or tablespoon is not an adequate measuring device and should not be used. TRILEPTAL oral suspension can be mixed in a small glass of water just prior to administration, or alternatively, may be swallowed directly from the syringe. After each use, close the bottle and rinse the syringe with warm water, and allow it to dry thoroughly.

TRILEPTAL oral suspension and TRILEPTAL film-coated tablets may be substituted at equal doses.

3 DOSAGE FORMS AND STRENGTHS

Film-coated Tablets:

- 150 mg: pale grey-green, ovaloid, slightly biconvex, scored on both sides. Imprinted with “T/D” on one side and “C/G” on the other side.
- 300 mg: yellow, ovaloid, slightly biconvex, scored on both sides. Imprinted with “TE/TE” on one side and “CG/CG” on the other side.
- 600 mg: light pink, ovaloid, slightly biconvex, scored on both sides. Imprinted with “TF/TF” on one side and “CG/CG” on the other side.

Oral Suspension:

- 300 mg/5 mL (60 mg/mL): off-white to slightly brown or slightly red suspension.

4 CONTRAINDICATIONS

TRILEPTAL is contraindicated in patients with a known hypersensitivity to oxcarbazepine or to any of its components, or to eslicarbazepine acetate [see Warnings and Precautions (5.2, 5.3)].

5 WARNINGS AND PRECAUTIONS

5.1 Hyponatremia

Clinically significant hyponatremia (sodium < 125 mmol/L) can develop during TRILEPTAL use. In the 14 controlled epilepsy studies, 2.5% of TRILEPTAL-treated patients (38/1524) had a sodium of less than 125 mmol/L at some point during treatment, compared to no such patients assigned placebo or active control (carbamazepine and phenobarbital for adjunctive and monotherapy substitution studies, and phenytoin and valproate for the monotherapy initiation studies). Clinically significant hyponatremia generally occurred during the first 3 months of treatment with TRILEPTAL, although there were patients who first developed a serum sodium < 125 mmol/L more than 1 year after initiation of therapy. Most patients who developed hyponatremia were asymptomatic, but patients in the clinical trials were frequently monitored and some had their TRILEPTAL dose reduced, discontinued, or had their fluid intake restricted for hyponatremia. Whether or not these maneuvers prevented the occurrence of more severe events is unknown. Cases of symptomatic hyponatremia and syndrome of inappropriate antidiuretic hormone secretion (SIADH) have been reported during postmarketing use. In clinical trials, patients whose treatment with TRILEPTAL was discontinued due to hyponatremia generally experienced normalization of serum sodium within a few days without additional treatment.

Measurement of serum sodium levels should be considered for patients during maintenance treatment with TRILEPTAL, particularly if the patient is receiving other medications known to decrease serum sodium levels (e.g., drugs associated with inappropriate ADH secretion), or if symptoms possibly indicating hyponatremia develop (e.g., nausea, malaise, headache, lethargy, confusion, obtundation, or increase in seizure frequency or severity).

5.2 Anaphylactic Reactions and Angioedema

Rare cases of anaphylaxis and angioedema involving the larynx, glottis, lips and eyelids have been reported in patients after taking the first or subsequent doses of TRILEPTAL. Angioedema associated with laryngeal edema can be fatal. If a patient develops any of these reactions after treatment with TRILEPTAL, the drug should be discontinued and an alternative treatment started. These patients should not be rechallenged with the drug [see Warnings and Precautions (5.3)].

5.3 Cross Hypersensitivity Reaction to Carbamazepine

Approximately 25% to 30% of patients who have had hypersensitivity reactions to carbamazepine will experience hypersensitivity reactions with TRILEPTAL. For this reason, patients should be specifically questioned about any prior experience with carbamazepine, and patients with a history of hypersensitivity reactions to carbamazepine should ordinarily be treated with TRILEPTAL only if the potential benefit justifies the potential risk. If signs or symptoms of hypersensitivity develop, TRILEPTAL should be discontinued immediately [see Warnings and Precautions (5.2, 5.8)].

5.4 Serious Dermatological Reactions

Serious dermatological reactions, including Stevens-Johnson syndrome (SJS) and toxic epidermal necrolysis (TEN), have been reported in both children and adults in association with TRILEPTAL use. Such serious skin reactions may be life threatening, and some patients have required hospitalization with very rare reports of fatal outcome. The median time of onset for reported cases was 19 days after treatment initiation. Recurrence of the serious skin reactions following rechallenge with TRILEPTAL has also been reported.

The reporting rate of TEN and SJS associated with TRILEPTAL use, which is generally accepted to be an underestimate due to underreporting, exceeds the background incidence rate estimates by a factor of 3- to 10-fold. Estimates of the background incidence rate for these serious skin reactions in the general population range between 0.5 to 6 cases per million-person years. Therefore, if a patient develops a skin reaction while taking TRILEPTAL, consideration should be given to discontinuing TRILEPTAL use and prescribing another antiepileptic medication.

Association With HLA-B*1502

Patients carrying the HLA-B*1502 allele may be at increased risk for SJS/TEN with TRILEPTAL treatment. Human Leukocyte Antigen (HLA) allele B*1502 increases the risk for developing SJS/TEN in patients treated with carbamazepine. The chemical structure of TRILEPTAL is similar to that of carbamazepine. Available clinical evidence, and data from nonclinical studies showing a direct interaction between TRILEPTAL and HLA-B*1502 protein, suggest that the HLA-B*1502 allele may also increase the risk for SJS/TEN with TRILEPTAL.

The frequency of HLA-B*1502 allele ranges from 2% to 12% in Han Chinese populations, is about 8% in Thai populations, and above 15% in the Philippines, and in some Malaysian populations. Allele frequencies up to about 2% and 6% have been reported in Korea and India, respectively. The frequency of the HLA-B*1502 allele is negligible in people from European descent, several African populations, indigenous peoples of the Americas, Hispanic populations, and in Japanese (< 1%).

Testing for the presence of the HLA-B*1502 allele should be considered in patients with ancestry in genetically at-risk populations, prior to initiating treatment with TRILEPTAL. The use of TRILEPTAL should be avoided in patients positive for HLA-B*1502 unless the benefits clearly outweigh the risks. Consideration should also be given to avoid the use of other drugs associated with SJS/TEN in HLA-B*1502 positive patients, when alternative therapies are otherwise equally acceptable. Screening is not generally recommended in patients from populations in which the prevalence of HLA-B*1502 is low, or in current TRILEPTAL users, as the risk of SJS/TEN is largely confined to the first few months of therapy, regardless of HLA-B*1502 status.

The use of HLA-B*1502 genotyping has important limitations, and must never substitute for appropriate clinical vigilance and patient management. The role of other possible factors in the development of, and morbidity from, SJS/TEN, such as AED dose, compliance, concomitant medications, comorbidities, and the level of dermatologic monitoring have not been well characterized.

5.5 Suicidal Behavior and Ideation

Antiepileptic drugs, including TRILEPTAL, increase the risk of suicidal thoughts or behavior in patients taking these drugs for any indication. Patients treated with any AED for any indication should be monitored for the emergence or worsening of depression, suicidal thoughts or behavior, and/or any unusual changes in mood or behavior.

Pooled analyses of 199 placebo-controlled clinical trials (mono- and adjunctive therapy) of 11 different AEDs showed that patients randomized to one of the AEDs had approximately twice the risk (adjusted Relative Risk 1.8, 95% CI:1.2, 2.7) of suicidal thinking or behavior compared to patients randomized to placebo. In these trials, which had a median treatment duration of 12 weeks, the estimated incidence rate of suicidal behavior or ideation among 27,863 AED-treated patients was 0.43%, compared to 0.24% among 16,029 placebo-treated patients, representing an increase of approximately one case of suicidal thinking or behavior for every 530 patients treated. There were 4 suicides in drug-treated patients in the trials and none in placebo-treated patients, but the number is too small to allow any conclusion about drug effect on suicide.

The increased risk of suicidal thoughts or behavior with AEDs was observed as early as one week after starting drug treatment with AEDs, and persisted for the duration of treatment assessed. Because most trials included in the analysis did not extend beyond 24 weeks, the risk of suicidal thoughts or behavior beyond 24 weeks could not be assessed.

The risk of suicidal thoughts or behavior was generally consistent among drugs in the data analyzed. The finding of increased risk with AEDs of varying mechanisms of action and across a range of indications suggests that the risk applies to all AEDs used for any indication. The risk did not vary substantially by age (5 to 100 years) in the clinical trials analyzed. Table 2 shows absolute and relative risk by indication for all evaluated AEDs.

Table 2: Risk by Indication for Antiepileptic Drugs in the Pooled Analysis
Indication | Placebo patients with events per 1000 patients | Drug patients with events per 1000 patients | Relative risk: incidence of events in drug patients/incidence in placebo patients | Risk difference: additional drug patients with events per 1000 patients
Epilepsy | 1.0 | 3.4 | 3.5 | 2.4
Psychiatric | 5.7 | 8.5 | 1.5 | 2.9
Other | 1.0 | 1.8 | 1.9 | 0.9
Total | 2.4 | 4.3 | 1.8 | 1.9

The relative risk for suicidal thoughts or behavior was higher in clinical trials for epilepsy than in clinical trials for psychiatric or other conditions, but the absolute risk differences were similar for the epilepsy and psychiatric indications.

Anyone considering prescribing TRILEPTAL or any other AED must balance the risk of suicidal thoughts or behavior with the risk of untreated illness. Epilepsy and many other illnesses for which AEDs are prescribed are themselves associated with morbidity and mortality and an increased risk of suicidal thoughts and behavior. Should suicidal thoughts and behavior emerge during treatment, the prescriber needs to consider whether the emergence of these symptoms in any given patient may be related to the illness being treated.

Patients, their caregivers, and families should be informed that AEDs increase the risk of suicidal thoughts and behavior and should be advised of the need to be alert for the emergence or worsening of the signs and symptoms of depression, any unusual changes in mood or behavior, or the emergence of suicidal thoughts, behavior, or thoughts about self-harm. Behaviors of concern should be reported immediately to healthcare providers.

5.6 Withdrawal of Antiepileptic Drugs

As with most AEDs, TRILEPTAL should generally be withdrawn gradually because of the risk of increased seizure frequency and status epilepticus [see Dosage and Administration (2.4) and Clinical Studies (14)]. But if withdrawal is needed because of a serious adverse event, rapid discontinuation can be considered.

5.7 Cognitive/Neuropsychiatric Adverse Reactions

Use of TRILEPTAL has been associated with CNS-related adverse reactions. The most significant of these can be classified into three general categories: 1) cognitive symptoms, including psychomotor slowing, difficulty with concentration, and speech or language problems; 2) somnolence or fatigue; and 3) coordination abnormalities, including ataxia and gait disturbances.

Patients should be monitored for these signs and symptoms and advised not to drive or operate machinery until they have gained sufficient experience on TRILEPTAL to gauge whether it adversely affects their ability to drive or operate machinery.

Adult Patients

In one large, fixed-dose study, TRILEPTAL was added to existing AED therapy (up to three concomitant AEDs). By protocol, the dosage of the concomitant AEDs could not be reduced as TRILEPTAL was added, reduction in TRILEPTAL dosage was not allowed if intolerance developed, and patients were discontinued if unable to tolerate their highest target maintenance doses. In this trial, 65% of patients were discontinued because they could not tolerate the 2400 mg/day dose of TRILEPTAL on top of existing AEDs. The adverse events seen in this study were primarily CNS related and the risk for discontinuation was dose related.

In this trial, 7.1% of oxcarbazepine-treated patients and 4% of placebo-treated patients experienced a cognitive adverse reaction. The risk of discontinuation for these events was about 6.5 times greater on oxcarbazepine than on placebo. In addition, 26% of oxcarbazepine-treated patients and 12% of placebo-treated patients experienced somnolence. The risk of discontinuation for somnolence was about 10 times greater on oxcarbazepine than on placebo. Finally, 28.7% of oxcarbazepine-treated patients and 6.4% of placebo-treated patients experienced ataxia or gait disturbances. The risk for discontinuation for these events was about 7 times greater on oxcarbazepine than on placebo.

In a single placebo-controlled monotherapy trial evaluating 2400 mg/day of TRILEPTAL, no patients in either treatment group discontinued double-blind treatment because of cognitive adverse events, somnolence, ataxia, or gait disturbance.

In the 2 dose-controlled conversion to monotherapy trials comparing 2400 mg/day and 300 mg/day TRILEPTAL, 1.1% of patients in the 2400 mg/day group discontinued double-blind treatment because of somnolence or cognitive adverse reactions compared to 0% in the 300 mg/day group. In these trials, no patients discontinued because of ataxia or gait disturbances in either treatment group.

Pediatric Patients

A study was conducted in pediatric patients (3 to 17 years old) with inadequately controlled partial-onset seizures in which TRILEPTAL was added to existing AED therapy (up to 2 concomitant AEDs). By protocol, the dosage of concomitant AEDs could not be reduced as TRILEPTAL was added. TRILEPTAL was titrated to reach a target dose ranging from 30 mg/kg to 46 mg/kg (based on a patient’s body weight with fixed doses for predefined weight ranges).

Cognitive adverse events occurred in 5.8% of oxcarbazepine-treated patients (the single most common event being concentration impairment, 4 of 138 patients) and in 3.1% of patients treated with placebo. In addition, 34.8% of oxcarbazepine-treated patients and 14.0% of placebo-treated patients experienced somnolence (no patient discontinued due to a cognitive adverse reaction or somnolence). Finally, 23.2% of oxcarbazepine-treated patients and 7.0% of placebo-treated patients experienced ataxia or gait disturbances. Two (1.4%) oxcarbazepine-treated patients and 1 (0.8%) placebo-treated patient discontinued due to ataxia or gait disturbances.

5.8 Drug Reaction With Eosinophilia and Systemic Symptoms/Multi-Organ Hypersensitivity

Drug Reaction with Eosinophilia and Systemic Symptoms (DRESS), also known as multi-organ hypersensitivity, has occurred with TRILEPTAL. Some of these events have been fatal or life-threatening. DRESS typically, although not exclusively, presents with fever, rash, lymphadenopathy and/or facial swelling, in association with other organ system involvement, such as hepatitis, nephritis, hematologic abnormalities, myocarditis, or myositis sometimes resembling an acute viral infection. Eosinophilia is often present. This disorder is variable in its expression, and other organ systems not noted here may be involved. It is important to note that early manifestations of hypersensitivity (e.g., fever, lymphadenopathy) may be present even though rash is not evident. If such signs or symptoms are present, the patient should be evaluated immediately. TRILEPTAL should be discontinued if an alternative etiology for the signs or symptoms cannot be established.

5.9 Hematologic Events

Rare reports of pancytopenia, agranulocytosis, and leukopenia have been seen in patients treated with TRILEPTAL during postmarketing experience. Discontinuation of the drug should be considered if any evidence of these hematologic events develops.

5.10 Seizure Control During Pregnancy

Due to physiological changes during pregnancy, plasma levels of the active metabolite of oxcarbazepine, the 10-monohydroxy derivative (MHD), may gradually decrease throughout pregnancy. It is recommended that patients be monitored carefully during pregnancy. Close monitoring should continue through the postpartum period because MHD levels may return after delivery.

5.11 Risk of Seizure Aggravation

Exacerbation of or new onset primary generalized seizures has been reported with TRILEPTAL. The risk of aggravation of primary generalized seizures is seen especially in children but may also occur in adults. In case of seizure aggravation, TRILEPTAL should be discontinued.

6 ADVERSE REACTIONS

The following serious adverse reactions are described below and elsewhere in the labeling:

- Hyponatremia [see Warnings and Precautions (5.1)]
- Anaphylactic Reactions and Angioedema [see Warnings and Precautions (5.2)]
- Cross Hypersensitivity Reaction to Carbamazepine [see Warnings and Precautions (5.3)]
- Serious Dermatological Reactions [see Warnings and Precautions (5.4)]
- Suicidal Behavior and Ideation [see Warnings and Precautions (5.5)]
- Cognitive/Neuropsychiatric Adverse Reactions [see Warnings and Precautions (5.7)]
- Drug Reaction with Eosinophilia and Systemic Symptoms (DRESS)/Multi-Organ Hypersensitivity [see Warnings and Precautions (5.8)]
- Hematologic Events [see Warnings and Precautions (5.9)]

6.1 Clinical Trials Experience

Because clinical trials are conducted under widely varying conditions, adverse reaction rates observed in the clinical trials of a drug cannot be directly compared to rates in the clinical trials of another drug and may not reflect the rates observed in practice.

Most Common Adverse Reactions in All Clinical Studies

Adjunctive Therapy/Monotherapy in Adults Previously Treated With Other AEDs

The most common (≥ 10% more than placebo for adjunctive or low dose for monotherapy) adverse reactions with TRILEPTAL: dizziness, somnolence, diplopia, fatigue, nausea, vomiting, ataxia, abnormal vision, headache, nystagmus tremor, and abnormal gait.

Approximately 23% of these 1537 adult patients discontinued treatment because of an adverse reaction. The adverse reactions most commonly associated with discontinuation were: dizziness (6.4%), diplopia (5.9%), ataxia (5.2%), vomiting (5.1%), nausea (4.9%), somnolence (3.8%), headache (2.9%), fatigue (2.1%), abnormal vision (2.1%), tremor (1.8%), abnormal gait (1.7%), rash (1.4%), and hyponatremia (1.0%).

Monotherapy in Adults Not Previously Treated With Other AEDs

The most common (≥ 5%) adverse reactions with TRILEPTAL in these patients were similar to those in previously treated patients.

Approximately 9% of these 295 adult patients discontinued treatment because of an adverse reaction. The adverse reactions most commonly associated with discontinuation were: dizziness (1.7%), nausea (1.7%), rash (1.7%), and headache (1.4%).

Adjunctive Therapy/Monotherapy in Pediatric Patients 4 Years Old and Above Previously Treated With Other AEDs

The most common (≥ 5%) adverse reactions with TRILEPTAL in these patients were similar to those seen in adults.

Approximately 11% of these 456 pediatric patients discontinued treatment because of an adverse reaction. The adverse reactions most commonly associated with discontinuation were: somnolence (2.4%), vomiting (2.0%), ataxia (1.8%), diplopia (1.3%), dizziness (1.3%), fatigue (1.1%), and nystagmus (1.1%).

Monotherapy in Pediatric Patients 4 Years Old and Above Not Previously Treated With Other AEDs

The most common (≥ 5%) adverse reactions with TRILEPTAL in these patients were similar to those in adults.

Approximately 9.2% of 152 pediatric patients discontinued treatment because of an adverse reaction. The adverse reactions most commonly associated (≥ 1%) with discontinuation were rash (5.3%) and maculopapular rash (1.3%).

Adjunctive Therapy/Monotherapy in Pediatric Patients 1 Month to < 4 Years Old Previously Treated or Not Previously Treated with Other AEDs:

The most common (≥ 5%) adverse reactions with TRILEPTAL in these patients were similar to those seen in older children and adults, except for infections and infestations which were more frequently seen in these younger children.

Approximately 11% of these 241 pediatric patients discontinued treatment because of an adverse reaction. The adverse reactions most commonly associated with discontinuation were: convulsions (3.7%), status epilepticus (1.2%), and ataxia (1.2%).

Controlled Clinical Studies of Adjunctive Therapy/Monotherapy in Adults Previously Treated With Other AEDs

Table 3 lists adverse reactions that occurred in at least 2% of adult patients with epilepsy, treated with TRILEPTAL or placebo as adjunctive treatment and were numerically more common in the patients treated with any dose of TRILEPTAL.

Table 4 lists adverse reactions in patients converted from other AEDs to either high-dose TRILEPTAL (2400 mg/day) or low-dose (300 mg/day) TRILEPTAL. Note that in some of these monotherapy studies patients who dropped out during a preliminary tolerability phase are not included in the tables.

Table 3: Adverse Reactions in a Controlled Clinical Study of Adjunctive Therapy With TRILEPTAL in Adults
 | TRILEPTAL dosage (mg/day)
Body system/ Adverse reaction | TRILEPTAL 600 N = 163 % | TRILEPTAL 1200 N = 171 % | TRILEPTAL 2400 N = 126 % | Placebo N = 166 %
Body as a whole
Fatigue | 15 | 12 | 15 | 7
Asthenia | 6 | 3 | 6 | 5
Leg edema | 2 | 1 | 2 | 1
Increased weight | 1 | 2 | 2 | 1
Feeling abnormal | 0 | 1 | 2 | 0
Cardiovascular system
Hypotension | 0 | 1 | 2 | 0
Digestive system
Nausea | 15 | 25 | 29 | 10
Vomiting | 13 | 25 | 36 | 5
Abdominal pain | 10 | 13 | 11 | 5
Diarrhea | 5 | 6 | 7 | 6
Dyspepsia | 5 | 5 | 6 | 2
Constipation | 2 | 2 | 6 | 4
Gastritis | 2 | 1 | 2 | 1
Metabolic and nutritional disorders
Hyponatremia | 3 | 1 | 2 | 1
Musculoskeletal system
Muscle weakness | 1 | 2 | 2 | 0
Sprains and strains | 0 | 2 | 2 | 1
Nervous system
Headache | 32 | 28 | 26 | 23
Dizziness | 26 | 32 | 49 | 13
Somnolence | 20 | 28 | 36 | 12
Ataxia | 9 | 17 | 31 | 5
Nystagmus | 7 | 20 | 26 | 5
Abnormal gait | 5 | 10 | 17 | 1
Insomnia | 4 | 2 | 3 | 1
Tremor | 3 | 8 | 16 | 5
Nervousness | 2 | 4 | 2 | 1
Agitation | 1 | 1 | 2 | 1
Abnormal coordination | 1 | 3 | 2 | 1
Abnormal EEG | 0 | 0 | 2 | 0
Speech disorder | 1 | 1 | 3 | 0
Confusion | 1 | 1 | 2 | 1
Cranial injury NOS | 1 | 0 | 2 | 1
Dysmetria | 1 | 2 | 3 | 0
Abnormal thinking | 0 | 2 | 4 | 0
Respiratory system
Rhinitis | 2 | 4 | 5 | 4
Skin and appendages
Acne | 1 | 2 | 2 | 0
Special senses
Diplopia | 14 | 30 | 40 | 5
Vertigo | 6 | 12 | 15 | 2
Abnormal vision | 6 | 14 | 13 | 4
Abnormal accommodation | 0 | 0 | 2 | 0
Abbreviations: EEG, electroencephalogram; NOS, not otherwise specified.

Table 4: Adverse Reactions in Controlled Clinical Studies of Monotherapy With TRILEPTAL in Adults Previously Treated With Other Antiepileptic Drugs
Body system/ Adverse reaction | TRILEPTAL dosage (mg/day)
 | TRILEPTAL 2400 mg/day N = 86 % | TRILEPTAL 300 mg/day N = 86 %
Body as a whole
Fatigue | 21 | 5
Fever | 3 | 0
Allergy | 2 | 0
Generalized edema | 2 | 1
Chest pain | 2 | 0
Digestive system
Nausea | 22 | 7
Vomiting | 15 | 5
Diarrhea | 7 | 5
Dyspepsia | 6 | 1
Anorexia | 5 | 3
Abdominal pain | 5 | 3
Dry mouth | 3 | 0
Hemorrhage rectum | 2 | 0
Toothache | 2 | 1
Hemic and lymphatic system
Lymphadenopathy | 2 | 0
Infections and infestations
Viral infection | 7 | 5
Infection | 2 | 0
Metabolic and nutritional disorders
Hyponatremia | 5 | 0
Thirst | 2 | 0
Nervous system
Headache | 31 | 15
Dizziness | 28 | 8
Somnolence | 19 | 5
Anxiety | 7 | 5
Ataxia | 7 | 1
Confusion | 7 | 0
Nervousness | 7 | 0
Insomnia | 6 | 3
Tremor | 6 | 3
Amnesia | 5 | 1
Aggravated convulsions | 5 | 2
Emotional lability | 3 | 2
Hypoesthesia | 3 | 1
Abnormal coordination | 2 | 1
Nystagmus | 2 | 0
Speech disorder | 2 | 0
Respiratory system
Upper respiratory tract infection | 10 | 5
Coughing | 5 | 0
Bronchitis | 3 | 0
Pharyngitis | 3 | 0
Skin and appendages
Hot flushes | 2 | 1
Purpura | 2 | 0
Special senses
Abnormal vision | 14 | 2
Diplopia | 12 | 1
Taste perversion | 5 | 0
Vertigo | 3 | 0
Earache | 2 | 1
Ear infection NOS | 2 | 0
Urogenital and reproductive system
Urinary tract infection | 5 | 1
Micturition frequency | 2 | 1
Vaginitis | 2 | 0
Abbreviation: NOS, not otherwise specified.

Controlled Clinical Study of Monotherapy in Adults Not Previously Treated With Other AEDs

Table 5 lists adverse reactions in a controlled clinical study of monotherapy in adults not previously treated with other AEDs that occurred in at least 2% of adult patients with epilepsy treated with TRILEPTAL or placebo and were numerically more common in the patients treated with TRILEPTAL.

Table 5: Adverse Reactions in a Controlled Clinical Study of Monotherapy With TRILEPTAL in Adults Not Previously Treated With Other Antiepileptic Drugs
Body system/ Adverse reaction | TRILEPTAL N = 55 % | Placebo N = 49 %
Body as a whole
Falling down NOS | 4 | 0
Digestive system
Nausea | 16 | 12
Diarrhea | 7 | 2
Vomiting | 7 | 6
Constipation | 5 | 0
Dyspepsia | 5 | 4
Musculoskeletal system
Back pain | 4 | 2
Nervous system
Dizziness | 22 | 6
Headache | 13 | 10
Ataxia | 5 | 0
Nervousness | 5 | 2
Amnesia | 4 | 2
Abnormal coordination | 4 | 2
Tremor | 4 | 0
Respiratory system
Upper respiratory tract infection | 7 | 0
Epistaxis | 4 | 0
Infection chest | 4 | 0
Sinusitis | 4 | 2
Skin and appendages
Rash | 4 | 2
Special senses
Vision abnormal | 4 | 0
Abbreviation: NOS, not otherwise specified.

Controlled Clinical Studies of Adjunctive Therapy/Monotherapy in Pediatric Patients Previously Treated With Other AEDs

Table 6 lists adverse reactions that occurred in at least 2% of pediatric patients with epilepsy treated with TRILEPTAL or placebo as adjunctive treatment and were numerically more common in the patients treated with TRILEPTAL.

Table 6: Adverse Reactions in Controlled Clinical Studies of Adjunctive Therapy/Monotherapy With TRILEPTAL in Pediatric Patients Previously Treated With Other Antiepileptic Drugs
Body system/ Adverse reaction | TRILEPTAL N = 171 % | Placebo N = 139 %
Body as a whole
Fatigue | 13 | 9
Allergy | 2 | 0
Asthenia | 2 | 1
Digestive system
Vomiting | 33 | 14
Nausea | 19 | 5
Constipation | 4 | 1
Dyspepsia | 2 | 0
Nervous system
Headache | 31 | 19
Somnolence | 31 | 13
Dizziness | 28 | 8
Ataxia | 13 | 4
Nystagmus | 9 | 1
Emotional lability | 8 | 4
Abnormal gait | 8 | 3
Tremor | 6 | 4
Speech disorder | 3 | 1
Impaired concentration | 2 | 1
Convulsions | 2 | 1
Involuntary muscle contractions | 2 | 1
Respiratory system
Rhinitis | 10 | 9
Pneumonia | 2 | 1
Skin and appendages
Bruising | 4 | 2
Increased sweating | 3 | 0
Special senses
Diplopia | 17 | 1
Abnormal vision | 13 | 1
Vertigo | 2 | 0

Other Events Observed in Association With the Administration of TRILEPTAL

In the paragraphs that follow, the adverse reactions, other than those in the preceding tables or text, that occurred in a total of 565 children and 1574 adults exposed to TRILEPTAL and that are reasonably likely to be related to drug use are presented. Events common in the population, events reflecting chronic illness and events likely to reflect concomitant illness are omitted particularly if minor. They are listed in order of decreasing frequency. Because the reports cite events observed in open label and uncontrolled trials, the role of TRILEPTAL in their causation cannot be reliably determined.

Body as a Whole: fever, malaise, pain chest precordial, rigors, weight decrease

Cardiovascular System: bradycardia, cardiac failure, cerebral hemorrhage, hypertension, hypotension postural, palpitation, syncope, tachycardia

Digestive System: appetite increased, blood in stool, cholelithiasis, colitis, duodenal ulcer, dysphagia, enteritis, eructation, esophagitis, flatulence, gastric ulcer, gingival bleeding, gum hyperplasia, hematemesis, hemorrhage rectum, hemorrhoids, hiccup, mouth dry, pain biliary, pain right hypochondrium, retching, sialoadenitis, stomatitis, stomatitis ulcerative

Hematologic and Lymphatic System: thrombocytopenia

Laboratory Abnormality: gamma-GT increased, hyperglycemia, hypocalcemia, hypoglycemia, hypokalemia, liver enzymes elevated, serum transaminase increased

Musculoskeletal System: hypertonia muscle

Nervous System: aggressive reaction, amnesia, anguish, anxiety, apathy, aphasia, aura, convulsions aggravated, delirium, delusion, depressed level of consciousness, dysphonia, dystonia, emotional lability, euphoria, extrapyramidal disorder, feeling drunk, hemiplegia, hyperkinesia, hyperreflexia, hypoesthesia, hypokinesia, hyporeflexia, hypotonia, hysteria, libido decreased, libido increased, manic reaction, migraine, muscle contractions involuntary, nervousness, neuralgia, oculogyric crisis, panic disorder, paralysis, paroniria, personality disorder, psychosis, ptosis, stupor, tetany

Respiratory System: asthma, dyspnea, epistaxis, laryngismus, pleurisy

Skin and Appendages: acne, alopecia, angioedema, bruising, dermatitis contact, eczema, facial rash, flushing, folliculitis, heat rash, hot flushes, photosensitivity reaction, pruritus genital, psoriasis, purpura, rash erythematous, rash maculopapular, vitiligo, urticaria

Special Senses: accommodation abnormal, cataract, conjunctival hemorrhage, edema eye, hemianopia, mydriasis, otitis externa, photophobia, scotoma, taste perversion, tinnitus, xerophthalmia

Surgical and Medical Procedures: procedure dental oral, procedure female reproductive, procedure musculoskeletal, procedure skin

Urogenital and Reproductive System: dysuria, hematuria, intermenstrual bleeding, leukorrhea, menorrhagia, micturition frequency, pain renal, pain urinary tract, polyuria, priapism, renal calculus

Other: Systemic lupus erythematosus

Laboratory Tests

Serum sodium levels below 125 mmol/L have been observed in patients treated with TRILEPTAL [see Warnings and Precautions (5.1)]. Experience from clinical trials indicates that serum sodium levels return toward normal when the TRILEPTAL dosage is reduced or discontinued, or when the patient was treated conservatively (e.g., fluid restriction).

Laboratory data from clinical trials suggest that TRILEPTAL use was associated with decreases in T4, without changes in T3 or TSH.

6.2 Postmarketing Experience

The following adverse reactions have been identified during postapproval use of TRILEPTAL. Because these reactions are reported voluntarily from a population of uncertain size, it is not always possible to reliably estimate their frequency or establish a causal relationship to drug exposure.

Body as a Whole: multi-organ hypersensitivity disorders characterized by features such as rash, fever, lymphadenopathy, abnormal liver function tests, eosinophilia and arthralgia [see Warnings and Precautions (5.8)]

Cardiovascular System: atrioventricular block

Immune System Disorders: anaphylaxis [see Warnings and Precautions (5.2)]

Digestive System: pancreatitis and/or lipase and/or amylase increase

Hematologic and Lymphatic Systems: aplastic anemia [see Warnings and Precautions (5.9)]

Metabolism and Nutrition Disorders: hypothyroidism and syndrome of inappropriate antidiuretic hormone secretion (SIADH)

Skin and Subcutaneous Tissue Disorders: erythema multiforme, Stevens-Johnson syndrome, toxic epidermal necrolysis [see Warnings and Precautions (5.4)], Acute Generalized Exanthematous Pustulosis (AGEP)

Musculoskeletal, Connective Tissue and Bone Disorders: There have been reports of decreased bone mineral density, osteoporosis, and fractures in patients on long-term therapy with TRILEPTAL.

Injury, Poisoning, and Procedural Complications: fall

Nervous System Disorders: dysarthria

7 DRUG INTERACTIONS

7.1 Effect of TRILEPTAL on Other Drugs

Phenytoin levels have been shown to increase with concomitant use of TRILEPTAL at doses greater than 1200 mg/day [see Clinical Pharmacology (12.3)]. Therefore, it is recommended that the plasma levels of phenytoin be monitored during the period of TRILEPTAL titration and dosage modification. A decrease in the dose of phenytoin may be required.

7.2 Effect of Other Drugs on TRILEPTAL

Strong inducers of cytochrome P450 enzymes and/or inducers of UGT (e.g., rifampin, carbamazepine, phenytoin and phenobarbital) have been shown to decrease the plasma/serum levels of MHD, the active metabolite of TRILEPTAL (25% to 49%) [see Clinical Pharmacology (12.3)]. If TRILEPTAL and strong CYP3A4 inducers, or UGT inducers are administered concurrently, it is recommended that the plasma levels of MHD be monitored during the period of TRILEPTAL titration. Dose adjustment of TRILEPTAL may be required after initiation, dosage modification, or discontinuation of such inducers.

7.3 Hormonal Contraceptives

Concurrent use of TRILEPTAL with hormonal contraceptives may render these contraceptives less effective [see Use in Specific Populations (8.3) and Clinical Pharmacology (12.3)]. Studies with other oral or implant contraceptives have not been conducted.

8 USE IN SPECIFIC POPULATIONS

8.1 Pregnancy

Pregnancy Exposure Registry

There is a pregnancy exposure registry that monitors pregnancy outcomes in women exposed to AEDs, such as TRILEPTAL, during pregnancy. Encourage women who are taking TRILEPTAL during pregnancy to enroll in the North American Antiepileptic Drug (NAAED) Pregnancy Registry by calling 1-888-233-2334 or visiting http://www.aedpregnancyregistry.org/.

Risk Summary

Although TRILEPTAL is closely related structurally to carbamazepine, which is considered to be teratogenic in humans, available human data from published literature and ongoing pregnancy registry studies on use of oxcarbazepine during pregnancy have not demonstrated an increased prevalence of major congenital malformations with first trimester exposure. However, all published studies reviewed have important methodological limitations, including unmeasured confounding and a small number of exposed cases (see Data). There are risks to the mother and fetus associated with partial onset seizures (see Clinical Considerations). There are no data on the risks associated with the use of TRILEPTAL and miscarriage or other adverse maternal outcomes.

Increased incidences of fetal structural abnormalities and other manifestations of developmental toxicity (embryolethality, growth retardation) were observed in the offspring of animals treated with either oxcarbazepine or its active 10-hydroxy metabolite (MHD) during pregnancy at doses similar to the maximum recommended human dose (MRHD).

In the U.S. general population, the estimated background risk of major birth defects and miscarriage in clinically recognized pregnancies is 2% to 4% and 15% to 20%, respectively. All pregnancies have a background risk of birth defect, loss, or other adverse outcomes.

Clinical Considerations

Disease-associated Maternal and/or Embryofetal Risk

Epilepsy, with or without exposure to antiepileptic drugs, has been associated with several adverse outcomes during pregnancy, including preeclampsia, preterm labor, antepartum and postpartum hemorrhage, placental abruption, poor fetal growth, prematurity, fetal death, and maternal mortality. The risk of maternal or fetal injury may be greatest for patients with untreated or poorly controlled convulsive seizures. Women with epilepsy who become pregnant should not abruptly discontinue antiepileptic drugs, including TRILEPTAL, due to the risk of status epilepticus or severe seizures, which may be life-threatening [see Warnings and Precautions (5.6)].

Maternal Adverse Reactions

An increase in seizure frequency may occur during pregnancy because of altered levels of the active metabolite of oxcarbazepine. Monitor patients carefully during pregnancy and through the postpartum period [see Warnings and Precautions (5.10)].

Data

Human Data

Data from a published retrospective cohort study and ongoing pregnancy registry studies on the use of oxcarbazepine during pregnancy have not demonstrated an increased prevalence of major congenital malformations with first trimester exposure. A retrospective cohort study conducted in Nordic countries (Denmark, Finland, Iceland, Norway, and Sweden) from 1996-2020 found that there was no increased prevalence of major congenital malformations when pregnancies exposed to oxcarbazepine during the first trimester were compared to pregnancies exposed to lamotrigine (adjusted risk ratio =1.09; 95% CI 0.83 to 1.44; n pregnancies exposed to oxcarbazepine= 1,313, n exposed cases = 58). In an ongoing pregnancy registry that included data from over 40 countries from 1999 to 2022 and 443 pregnancies exposed to oxcarbazepine, oxcarbazepine exposure during the first trimester was not associated with major congenital malformations (adjusted odds ratio =1.09; 95% CI 0.56 to 2.13, n exposed cases = 10). However, there are important methodological limitations of these studies including unmeasured confounding factors and a small number of exposed cases in the registry.

Animal Data

When pregnant rats were given oxcarbazepine (0, 30, 300, or 1000 mg/kg/day) orally throughout the period of organogenesis, increased incidences of fetal malformations (craniofacial, cardiovascular, and skeletal) and variations were observed at the intermediate and high doses (approximately 1.2 and 4 times, respectively, the MRHD on a mg/m^2 basis). Increased embryofetal death and decreased fetal body weights were seen at the high dose. Doses ≥ 300 mg/kg/day were also maternally toxic (decreased body weight gain, clinical signs), but there is no evidence to suggest that teratogenicity was secondary to the maternal effects.

In a study in which pregnant rabbits were orally administered MHD (0, 20, 100, or 200 mg/kg/day) during organogenesis, embryofetal mortality was increased at the highest dose (1.5 times the MRHD on a mg/m^2 basis). This dose produced only minimal maternal toxicity.

In a study in which female rats were dosed orally with oxcarbazepine (0, 25, 50, or 150 mg/kg/day) during the latter part of gestation and throughout the lactation period, a persistent reduction in body weights and altered behavior (decreased activity) were observed in offspring exposed to the highest dose (less than the MRHD on a mg/m^2 basis). Oral administration of MHD (0, 25, 75, or 250 mg/kg/day) to rats during gestation and lactation resulted in a persistent reduction in offspring weights at the highest dose (equivalent to the MRHD on a mg/m^2 basis).

8.2 Lactation

Risk Summary

Oxcarbazepine and its active metabolite (MHD) are present in human milk after TRILEPTAL administration. The effects of oxcarbazepine and its active metabolite (MHD) on the breastfed infant or on milk production are unknown. The developmental and health benefits of breastfeeding should be considered along with the mother’s clinical need for TRILEPTAL and any potential adverse effects on the breastfed infant from TRILEPTAL or from the underlying maternal condition.

8.3 Females and Males of Reproductive Potential

Contraception

Use of TRILEPTAL with hormonal contraceptives containing ethinylestradiol or levonorgestrel is associated with decreased plasma concentrations of these hormones and may result in a failure of the therapeutic effect of the oral contraceptive drug. Advise women of reproductive potential taking TRILEPTAL who are using a contraceptive containing ethinylestradiol or levonorgestrel to use additional or alternative non-hormonal birth control [see Drug Interactions (7.3) and Clinical Pharmacology (12.3)].

8.4 Pediatric Use

TRILEPTAL is indicated for use as adjunctive therapy for partial-onset seizures in patients aged 2 to 16 years.

The safety and effectiveness for use as adjunctive therapy for partial-onset seizures in pediatric patients below the age of 2 have not been established.

TRILEPTAL is also indicated as monotherapy for partial-onset seizures in patients aged 4 to 16 years.

The safety and effectiveness for use as monotherapy for partial-onset seizures in pediatric patients below the age of 4 have not been established.

TRILEPTAL has been given to 898 patients between the ages of 1 month to 17 years in controlled clinical trials (332 treated as monotherapy) and about 677 patients between the ages of 1 month to 17 years in other trials [see Warnings and Precautions (5.11), Adverse Reactions (6.1), Clinical Pharmacology (12.3), and Clinical Studies (14)].

8.5 Geriatric Use

There were 52 patients over age 65 in controlled clinical trials and 565 patients over the age of 65 in other trials. Following administration of single (300 mg) and multiple (600 mg/day) doses of TRILEPTAL in elderly volunteers (60 to 82 years of age), the maximum plasma concentrations and area under the curve (AUC) values of MHD were 30% to 60% higher than in younger volunteers (18 to 32 years of age). Comparisons of creatinine clearance in young and elderly volunteers indicate that the difference was due to age-related reductions in creatinine clearance. Close monitoring of sodium levels is required in elderly patients at risk for hyponatremia [see Warnings and Precautions (5.1)].

8.6 Renal Impairment

Dose adjustment is recommended for renally impaired patients (creatinine clearance < 30 mL/min) [see Dosage and Administration (2.7) and Clinical Pharmacology (12.3)].

9 DRUG ABUSE AND DEPENDENCE

9.2 Abuse

The abuse potential of TRILEPTAL has not been evaluated in human studies.

9.3 Dependence

Intragastric injections of oxcarbazepine to 4 cynomolgus monkeys demonstrated no signs of physical dependence as measured by the desire to self-administer oxcarbazepine by lever pressing activity.

10 OVERDOSAGE

10.1 Human Overdose Experience

Isolated cases of overdose with TRILEPTAL have been reported. The maximum dose taken was approximately 48,000 mg. All patients recovered with symptomatic treatment. Nausea, vomiting, somnolence, aggression, agitation, hypotension, and tremor each occurred in more than one patient. Coma, confusional state, convulsion, dyscoordination, depressed level of consciousness, diplopia, dizziness, dyskinesia, dyspnea, QT prolongation, headache, miosis, nystagmus, overdose, decreased urine output, and blurred vision also occurred.

10.2 Treatment and Management

There is no specific antidote. Symptomatic and supportive treatment should be administered as appropriate. Removal of the drug by gastric lavage and/or inactivation by administering activated charcoal should be considered.

11 DESCRIPTION

TRILEPTAL is an AED available as 150 mg, 300 mg, and 600 mg film-coated tablets for oral administration. TRILEPTAL is also available as a 300 mg/5 mL (60 mg/mL) oral suspension. Oxcarbazepine is 10,11-Dihydro-10-oxo-5H-dibenz[b,f]azepine-5-carboxamide, and its structural formula is:

Oxcarbazepine is a white to faintly orange crystalline powder. It is slightly soluble in chloroform, dichloromethane, acetone, and methanol and practically insoluble in ethanol, ether and water. Its molecular weight is 252.27 g/mol.

TRILEPTAL film-coated tablets contain the following inactive ingredients: colloidal silicon dioxide, crospovidone, hydroxypropyl methylcellulose, iron oxide, magnesium stearate, microcrystalline cellulose, polyethylene glycol, talc, and titanium dioxide.

TRILEPTAL oral suspension contains the following inactive ingredients: ascorbic acid; dispersible cellulose; ethanol; macrogol stearate; methyl parahydroxybenzoate; propylene glycol; propyl parahydroxybenzoate; purified water; sodium saccharin; sorbic acid; sorbitol; yellow-plum-lemon aroma.

12 CLINICAL PHARMACOLOGY

12.1 Mechanism of Action

The pharmacological activity of TRILEPTAL is primarily exerted through the 10-monohydroxy metabolite (MHD) of oxcarbazepine [see Clinical Pharmacology (12.3)]. The precise mechanism by which oxcarbazepine and MHD exert their anti-seizure effect is unknown; however, in vitro electrophysiological studies indicate that they produce blockade of voltage-sensitive sodium channels, resulting in stabilization of hyperexcited neural membranes, inhibition of repetitive neuronal firing, and diminution of propagation of synaptic impulses. These actions are thought to be important in the prevention of seizure spread in the intact brain. In addition, increased potassium conductance and modulation of high-voltage activated calcium channels may contribute to the anticonvulsant effects of the drug. No significant interactions of oxcarbazepine or MHD with brain neurotransmitter or modulator receptor sites have been demonstrated.

12.2 Pharmacodynamics

Oxcarbazepine and its active metabolite (MHD) exhibit anticonvulsant properties in animal seizure models. They protected rodents against electrically induced tonic extension seizures and, to a lesser degree, chemically induced clonic seizures, and abolished or reduced the frequency of chronically recurring focal seizures in Rhesus monkeys with aluminum implants. No development of tolerance (i.e., attenuation of anticonvulsive activity) was observed in the maximal electroshock test when mice and rats were treated daily for 5 days and 4 weeks, respectively, with oxcarbazepine or MHD.

12.3 Pharmacokinetics

Following oral administration of TRILEPTAL tablets, oxcarbazepine is completely absorbed and extensively metabolized to its pharmacologically active 10-monohydroxy metabolite (MHD). In a mass balance study in people, only 2% of total radioactivity in plasma was due to unchanged oxcarbazepine, with approximately 70% present as MHD, and the remainder attributable to minor metabolites.

The half-life of the parent is about 2 hours, while the half-life of MHD is about 9 hours, so that MHD is responsible for most antiepileptic activity.

Absorption

Based on MHD concentrations, TRILEPTAL tablets and suspension were shown to have similar bioavailability.

After single-dose administration of TRILEPTAL tablets to healthy male volunteers under fasted conditions, the median tmax was 4.5 (range, 3 to 13) hours. After single-dose administration of TRILEPTAL oral suspension to healthy male volunteers under fasted conditions, the median tmax was 6 hours.

Steady-state plasma concentrations of MHD are reached within 2 to 3 days in patients when TRILEPTAL is given twice a day. At steady state the pharmacokinetics of MHD are linear and show dose proportionality over the dose range of 300 to 2400 mg/day.

Food has no effect on the rate and extent of absorption of oxcarbazepine from TRILEPTAL tablets. Although not directly studied, the oral bioavailability of the TRILEPTAL suspension is unlikely to be affected under fed conditions. Therefore, TRILEPTAL tablets and suspension can be taken with or without food.

Distribution

The apparent volume of distribution of MHD is 49 L.

Approximately 40% of MHD is bound to serum proteins, predominantly to albumin. Binding is independent of the serum concentration within the therapeutically relevant range. Oxcarbazepine and MHD do not bind to alpha-1-acid glycoprotein.

Metabolism and Excretion

Oxcarbazepine is rapidly reduced by cytosolic enzymes in the liver to its 10-monohydroxy metabolite, MHD, which is primarily responsible for the pharmacological effect of TRILEPTAL. MHD is metabolized further by conjugation with glucuronic acid. Minor amounts (4% of the dose) are oxidized to the pharmacologically inactive 10,11-dihydroxy metabolite (DHD).

Oxcarbazepine is cleared from the body mostly in the form of metabolites which are predominantly excreted by the kidneys. More than 95% of the dose appears in the urine, with less than 1% as unchanged oxcarbazepine. Fecal excretion accounts for less than 4% of the administered dose. Approximately 80% of the dose is excreted in the urine either as glucuronides of MHD (49%) or as unchanged MHD (27%); the inactive DHD accounts for approximately 3% and conjugates of MHD and oxcarbazepine account for 13% of the dose.

The half-life of the parent is about 2 hours, while the half-life of MHD is about 9 hours.

Specific Populations

Geriatrics

Following administration of single (300 mg) and multiple (600 mg/day) doses of TRILEPTAL to elderly volunteers (60 to 82 years of age), the maximum plasma concentrations and AUC values of MHD were 30% to 60% higher than in younger volunteers (18 to 32 years of age). Comparisons of creatinine clearance in young and elderly volunteers indicate that the difference was due to age-related reductions in creatinine clearance.

Pediatrics

Weight-adjusted MHD clearance decreases as age and weight increases, approaching that of adults. The mean weight-adjusted clearance in children 2 years to < 4 years of age is approximately 80% higher on average than that of adults. Therefore, MHD exposure in these children is expected to be about one-half that of adults when treated with a similar weight-adjusted dose. The mean weight-adjusted clearance in children 4 to 12 years of age is approximately 40% higher on average than that of adults. Therefore, MHD exposure in these children is expected to be about three-quarters that of adults when treated with a similar weight-adjusted dose. As weight increases, for patients 13 years of age and above, the weight-adjusted MHD clearance is expected to reach that of adults.

Pediatric Patients With Obesity

A population PK analysis of oxcarbazepine was conducted that included n = 92 obese and non-obese pediatric patients < 18 years of age to evaluate the potential impact of obesity on plasma oxcarbazepine exposures. Obesity was defined as BMI ≥ 95th percentile for age and sex based on CDC 2000 growth chart recommendations. Simulated results from this analysis suggested that the target maintenance doses for oxcarbazepine, applied in pediatric patients ≥ 2 years of age, produced equivalent steady-state exposure of MHD between pediatric patients with and without obesity. This finding is consistent when using total body weight, or when using fat-free mass in patients ≥ 3 years and total body weight in patients < 3 years in the simulations. Dosage adjustment according to obesity status is not necessary.

Gender

No gender-related pharmacokinetic differences have been observed in children, adults, or the elderly.

Race

No specific studies have been conducted to assess what effect, if any, race may have on the disposition of oxcarbazepine.

Renal Impairment

There is a linear correlation between creatinine clearance and the renal clearance of MHD. When TRILEPTAL is administered as a single 300 mg dose in renally-impaired patients (creatinine clearance < 30 mL/min), the elimination half-life of MHD is prolonged to 19 hours, with a 2-fold increase in AUC [see Dosage and Administration (2.7) and Use in Specific Populations (8.6)].

Hepatic Impairment

The pharmacokinetics and metabolism of oxcarbazepine and MHD were evaluated in healthy volunteers and hepatically-impaired subjects after a single 900-mg oral dose. Mild-to-moderate hepatic impairment did not affect the pharmacokinetics of oxcarbazepine and MHD [see Dosage and Administration (2.8)].

Pregnancy

Due to physiological changes during pregnancy, MHD plasma levels may gradually decrease throughout pregnancy [see Use in Specific Populations (8.1)].

Drug Interactions:

- In Vitro

Oxcarbazepine can inhibit CYP2C19 and induce CYP3A4/5 with potentially important effects on plasma concentrations of other drugs. In addition, several AEDs that are cytochrome P450 inducers can decrease plasma concentrations of oxcarbazepine and MHD. No autoinduction has been observed with TRILEPTAL.

Oxcarbazepine was evaluated in human liver microsomes to determine its capacity to inhibit the major cytochrome P450 enzymes responsible for the metabolism of other drugs. Results demonstrate that oxcarbazepine and its pharmacologically active 10-monohydroxy metabolite (MHD) have little or no capacity to function as inhibitors for most of the human cytochrome P450 enzymes evaluated (CYP1A2, CYP2A6, CYP2C9, CYP2D6, CYP2E1, CYP4A9, and CYP4A11) with the exception of CYP2C19 and CYP3A4/5. Although inhibition of CYP3A4/5 by oxcarbazepine and MHD did occur at high concentrations, it is not likely to be of clinical significance. The inhibition of CYP2C19 by oxcarbazepine and MHD can cause increased plasma concentrations of drugs that are substrates of CYP2C19, which is clinically relevant.

In vitro, the UDP-glucuronyl transferase level was increased, indicating induction of this enzyme. Increases of 22% with MHD and 47% with oxcarbazepine were observed. As MHD, the predominant plasma substrate, is only a weak inducer of UDP-glucuronyl transferase, it is unlikely to have an effect on drugs that are mainly eliminated by conjugation through UDP-glucuronyl transferase (e.g., valproic acid, lamotrigine).

In addition, oxcarbazepine and MHD induce a subgroup of the cytochrome P450 3A family (CYP3A4 and CYP3A5) responsible for the metabolism of dihydropyridine calcium antagonists, oral contraceptives and cyclosporine resulting in a lower plasma concentration of these drugs.

As binding of MHD to plasma proteins is low (40%), clinically significant interactions with other drugs through competition for protein binding sites are unlikely.

- In Vivo

Other Antiepileptic Drugs

Potential interactions between TRILEPTAL and other AEDs were assessed in clinical studies. The effect of these interactions on mean AUCs and Cmin are summarized in Table 7 [see Drug Interactions (7.1, 7.2)].

Table 7: Summary of Antiepileptic Drug Interactions With TRILEPTAL
AED coadministered | Dose of AED (mg/day) | TRILEPTAL dose (mg/day) | Influence of TRILEPTAL on AED concentration (mean change, 90% confidence interval) | Influence of AED on MHD concentration (mean change, 90% confidence interval)
Carbamazepine | 400-2000 | 900 | nc^1 | 40% decrease [CI: 17% decrease, 57% decrease]
Phenobarbital | 100-150 | 600-1800 | 14% increase [CI: 2% increase, 24% increase] | 25% decrease [CI: 12% decrease, 51% decrease]
Phenytoin | 250-500 | 600-1800 > 1200-2400 | nc^1,2 up to 40% increase^3 [CI: 12% increase, 60% increase] | 30% decrease [CI: 3% decrease, 48% decrease]
Valproic acid | 400-2800 | 600-1800 | nc^1 | 18% decrease [CI: 13% decrease, 40% decrease]
Lamotrigine | 200 | 1200 | nc^1 | nc^1
Abbreviations: AED, antiepileptic drugs; CI, confidence interval; MHD, 10-monohydroxy derivative.
^1nc denotes a mean change of less than 10%.
^2Pediatrics.
^3Mean increase in adults at high TRILEPTAL doses.

Hormonal Contraceptives

Coadministration of TRILEPTAL with an oral contraceptive has been shown to influence the plasma concentrations of the two hormonal components: ethinylestradiol (EE) and levonorgestrel (LNG) [see Drug Interactions (7.3)]. The mean AUC values of EE were decreased by 48% [90% CI: 22 to 65] in one study and 52% [90% CI: 38 to 52] in another study. The mean AUC values of LNG were decreased by 32% [90% CI: 20 to 45] in one study and 52% [90% CI: 42 to 52] in another study.

Other Drug Interactions

Calcium Antagonists: After repeated coadministration of TRILEPTAL, the AUC of felodipine was lowered by 28% [90% CI: 20 to 33]. Verapamil produced a decrease of 20% [90% CI: 18 to 27] of the plasma levels of MHD.

Cimetidine, erythromycin and dextropropoxyphene had no effect on the pharmacokinetics of MHD. Results with warfarin show no evidence of interaction with either single or repeated doses of TRILEPTAL.

13 NONCLINICAL TOXICOLOGY

13.1 Carcinogenesis, Mutagenesis, Impairment of Fertility

Carcinogenesis

In 2-year carcinogenicity studies, oxcarbazepine was administered in the diet at doses of up to 100 mg/kg/day to mice and by gavage at doses of up to 250 mg/kg/day to rats, and the pharmacologically active 10-hydroxy metabolite (MHD) was administered orally at doses of up to 600 mg/kg/day to rats. In mice, a dose-related increase in the incidence of hepatocellular adenomas was observed at oxcarbazepine doses ≥ 70 mg/kg/day, which is less than the maximum recommended human dose (MRHD) on a mg/m^2 basis. In rats, the incidence of hepatocellular carcinomas was increased in females treated with oxcarbazepine at doses ≥ 25 mg/kg/day (less than the MRHD on a mg/m^2 basis), and incidences of hepatocellular adenomas and/or carcinomas were increased in males and females treated with MHD at doses of 600 mg/kg/day (2.4 times the MRHD on a mg/m^2 basis) and ≥ 250 mg/kg/day (equivalent to the MRHD on a mg/m^2 basis), respectively. There was an increase in the incidence of benign testicular interstitial cell tumors in rats at 250 mg oxcarbazepine/kg/day and at ≥ 250 mg MHD/kg/day, and an increase in the incidence of granular cell tumors in the cervix and vagina in rats at 600 mg MHD/kg/day.

Mutagenesis

Oxcarbazepine increased mutation frequencies in the in vitro Ames test in the absence of metabolic activation. Both oxcarbazepine and MHD produced increases in chromosomal aberrations and polyploidy in the Chinese hamster ovary assay in vitro in the absence of metabolic activation. MHD was negative in the Ames test, and no mutagenic or clastogenic activity was found with either oxcarbazepine or MHD in V79 Chinese hamster cells in vitro. Oxcarbazepine and MHD were both negative for clastogenic or aneugenic effects (micronucleus formation) in an in vivo rat bone marrow assay.

Impairment of Fertility

In a study in which male and female rats were administered oxcarbazepine (0, 25, 75, and 150 mg/kg/day) orally prior to and during mating and continuing in females during gestation, no adverse effects on fertility or reproductive performance were observed. The highest dose tested is less than the MRHD on a mg/m^2 basis. In a fertility study in which rats were administered MHD (0, 50, 150, or 450 mg/kg/day) orally prior to and during mating and early gestation, estrous cyclicity was disrupted and numbers of corpora lutea, implantations, and live embryos were reduced in females receiving the highest dose (approximately 2 times the MRHD on a mg/m^2 basis).

14 CLINICAL STUDIES

The effectiveness of TRILEPTAL as adjunctive and monotherapy for partial-onset seizures in adults, and as adjunctive therapy in children aged 2 to 16 years was established in seven multicenter, randomized, controlled trials.

The effectiveness of TRILEPTAL as monotherapy for partial-onset seizures in children aged 4 to 16 years was determined from data obtained in the studies described, as well as by pharmacokinetic/pharmacodynamic considerations.

14.1 TRILEPTAL Monotherapy Trials

Four randomized, controlled, double-blind, multicenter trials, conducted in a predominately adult population, demonstrated the efficacy of TRILEPTAL as monotherapy. Two trials compared TRILEPTAL to placebo and 2 trials used a randomized withdrawal design to compare a high dose (2400 mg) with a low dose (300 mg) of TRILEPTAL, after substituting TRILEPTAL 2400 mg/day for 1 or more AEDs. All doses were administered on a twice a day schedule. A fifth randomized, controlled, rater-blind, multicenter study, conducted in a pediatric population, failed to demonstrate a statistically significant difference between low- and high-dose TRILEPTAL-treatment groups.

One placebo-controlled trial was conducted in 102 patients (11 to 62 years of age) with refractory partial-onset seizures who had completed an inpatient evaluation for epilepsy surgery. Patients had been withdrawn from all AEDs and were required to have 2 to 10 partial-onset seizures within 48 hours prior to randomization. Patients were randomized to receive either placebo or TRILEPTAL given as 1500 mg/day on Day 1 and 2400 mg/day thereafter for an additional 9 days, or until 1 of the following 3 exit criteria occurred: 1) the occurrence of a fourth partial-onset seizure, excluding Day 1, 2) 2 new-onset secondarily generalized seizures, where such seizures were not seen in the 1-year period prior to randomization, or 3) occurrence of serial seizures or status epilepticus. The primary measure of effectiveness was a between-group comparison of the time to meet exit criteria. There was a statistically significant difference in favor of TRILEPTAL (see Figure 1), p = 0.0001.

Figure 1: Kaplan-Meier Estimates of Exit Rate by Treatment Group

The second placebo-controlled trial was conducted in 67 untreated patients (8 to 69 years of age) with newly-diagnosed and recent-onset partial seizures. Patients were randomized to placebo or TRILEPTAL, initiated at 300 mg twice a day and titrated to 1200 mg/day (given as 600 mg twice a day) in 6 days, followed by maintenance treatment for 84 days. The primary measure of effectiveness was a between-group comparison of the time to first seizure. The difference between the 2 treatments was statistically significant in favor of TRILEPTAL (see Figure 2), p = 0.046.

Figure 2: Kaplan-Meier Estimates of First Seizure Event Rate by Treatment Group

A third trial substituted TRILEPTAL monotherapy at 2400 mg/day for carbamazepine in 143 patients (12 to 65 years of age) whose partial-onset seizures were inadequately controlled on carbamazepine (CBZ) monotherapy at a stable dose of 800 to 1600 mg/day, and maintained this TRILEPTAL dose for 56 days (baseline phase). Patients who were able to tolerate titration of TRILEPTAL to 2400 mg/day during simultaneous carbamazepine withdrawal were randomly assigned to either 300 mg/day of TRILEPTAL or 2400 mg/day TRILEPTAL. Patients were observed for 126 days or until 1 of the following 4 exit criteria occurred: 1) a doubling of the 28-day seizure frequency compared to baseline, 2) a 2-fold increase in the highest consecutive 2-day seizure frequency during baseline, 3) a single generalized seizure if none had occurred during baseline, or 4) a prolonged generalized seizure. The primary measure of effectiveness was a between-group comparison of the time to meet exit criteria. The difference between the curves was statistically significant in favor of the TRILEPTAL 2400 mg/day group (see Figure 3), p = 0.0001.

Figure 3: Kaplan-Meier Estimates of Exit Rate by Treatment Group

Another monotherapy substitution trial was conducted in 87 patients (11 to 66 years of age) whose seizures were inadequately controlled on 1 or 2 AEDs. Patients were randomized to either TRILEPTAL 2400 mg/day or 300 mg/day and their standard AED regimen(s) were eliminated over the first 6 weeks of double-blind therapy. Double-blind treatment continued for another 84 days (total double-blind treatment of 126 days) or until 1 of the 4 exit criteria described for the previous study occurred. The primary measure of effectiveness was a between-group comparison of the percentage of patients meeting exit criteria. The results were statistically significant in favor of the TRILEPTAL 2400 mg/day group (14/34; 41.2%) compared to the TRILEPTAL 300 mg/day group (42/45; 93.3%) (p< 0.0001). The time to meeting one of the exit criteria was also statistically significant in favor of the TRILEPTAL 2400 mg/day group (see Figure 4), p = 0.0001.

Figure 4: Kaplan-Meier Estimates of Exit Rate by Treatment Group

A monotherapy trial was conducted in 92 pediatric patients (1 month to 16 years of age) with inadequately-controlled or new-onset partial seizures. Patients were hospitalized and randomized to either TRILEPTAL 10 mg/kg/day or were titrated up to 40 to 60 mg/kg/day within 3 days while withdrawing the previous AED on the second day of TRILEPTAL. Seizures were recorded through continuous video-EEG monitoring from Day 3 to Day 5. Patients either completed the 5-day treatment or met 1 of the 2 exit criteria: 1) three study-specific seizures (i.e., electrographic partial-onset seizures with a behavioral correlate), 2) a prolonged study-specific seizure. The primary measure of effectiveness was a between-group comparison of the time to meet exit criteria in which the difference between the curves was not statistically significant (p = 0.904). The majority of patients from both dose groups completed the 5-day study without exiting.

Although this study failed to demonstrate an effect of oxcarbazepine as monotherapy in pediatric patients, several design elements, including the short treatment and assessment period, the absence of a true placebo, and the likely persistence of plasma levels of previously administered AEDs during the treatment period, make the results uninterpretable. For this reason, the results do not undermine the conclusion, based on pharmacokinetic/pharmacodynamic considerations, that oxcarbazepine is effective as monotherapy in pediatric patients 4 years old and older.

14.2 TRILEPTAL Adjunctive Therapy Trials

The effectiveness of TRILEPTAL as an adjunctive therapy for partial-onset seizures was established in 2 multicenter, randomized, double-blind, placebo-controlled trials, one in 692 patients (15 to 66 years of age) and one in 264 pediatric patients (3 to 17 years of age), and in one multicenter, rater-blind, randomized, age-stratified, parallel-group study comparing 2 doses of oxcarbazepine in 128 pediatric patients (1 month to < 4 years of age).

Patients in the 2 placebo-controlled trials were on 1 to 3 concomitant AEDs. In both of the trials, patients were stabilized on optimum dosages of their concomitant AEDs during an 8-week baseline phase. Patients who experienced at least 8 (minimum of 1 to 4 per month) partial-onset seizures during the baseline phase were randomly assigned to placebo or to a specific dose of TRILEPTAL in addition to their other AEDs.

In these studies, the dose was increased over a 2-week period until either the assigned dose was reached, or intolerance prevented increases. Patients then entered a 14- (pediatrics) or 24-week (adults) maintenance period.

In the adult trial, patients received fixed doses of 600, 1200 or 2400 mg/day. In the pediatric trial, patients received maintenance doses in the range of 30 to 46 mg/kg/day, depending on baseline weight. The primary measure of effectiveness in both trials was a between-group comparison of the percentage change in partial-onset seizure frequency in the double-blind treatment phase relative to baseline phase. This comparison was statistically significant in favor of TRILEPTAL at all doses tested in both trials (p = 0.0001 for all doses for both trials). The number of patients randomized to each dose, the median baseline seizure rate, and the median percentage seizure rate reduction for each trial are shown in Table 8. It is important to note that in the high-dose group in the study in adults, over 65% of patients discontinued treatment because of adverse events; only 46 (27%) of the patients in this group completed the 28-week study [see Adverse Reactions (6)], an outcome not seen in the monotherapy studies.

Table 8: Summary of Percentage Change in Partial-Onset Seizure Frequency From Baseline for Placebo-Controlled Adjunctive Therapy Trials
Trial | Treatment group
 |  | N |  | Baseline median seizure rate* |  | Median % reduction
1 (pediatrics) | TRILEPTAL | 136 |  | 12.5 |  | 34.8^1
 | Placebo | 128 |  | 13.1 |  | 9.4
2 (adults) | TRILEPTAL 2400 mg/day | 174 |  | 10.0 |  | 49.9^1
 | TRILEPTAL 1200 mg/day | 177 |  | 9.8 |  | 40.2^1
 | TRILEPTAL 600 mg/day | 168 |  | 9.6 |  | 26.4^1
 | Placebo | 173 |  | 8.6 |  | 7.6
^1p = 0.0001.
* = number of seizures per 28 days.

Subset analyses of the antiepileptic efficacy of TRILEPTAL with regard to gender in these trials revealed no important differences in response between men and women. Because there were very few patients over the age of 65 years in controlled trials, the effect of the drug in the elderly has not been adequately assessed.

The third adjunctive therapy trial enrolled 128 pediatric patients (1 month to < 4 years of age) with inadequately-controlled partial-onset seizures on 1 to 2 concomitant AEDs. Patients who experienced at least 2 study-specific seizures (i.e., electrographic partial-onset seizures with a behavioral correlate) during the 72-hour baseline period were randomly assigned to either TRILEPTAL 10 mg/kg/day or were titrated up to 60 mg/kg/day within 26 days. Patients were maintained on their randomized target dose for 9 days and seizures were recorded through continuous video-EEG monitoring during the last 72 hours of the maintenance period. The primary measure of effectiveness in this trial was a between-group comparison of the change in seizure frequency per 24 hours compared to the seizure frequency at baseline. For the entire group of patients enrolled, this comparison was statistically significant in favor of TRILEPTAL 60 mg/kg/day. In this study, there was no evidence that TRILEPTAL was effective in patients below the age of 2 years (N = 75).

16 HOW SUPPLIED/STORAGE AND HANDLING

Tablets

150 mg Film-Coated Tablets: pale grey-green, ovaloid, slightly biconvex, scored on both sides. Imprinted with “T/D” on one side and “C/G” on the other side.

Bottle of 100……………………………………………………………………………………………...NDC 0078-0456-05

Unit Dose (blister pack)

Box of 100 (strips of 10)………………………………………………………………………………....NDC 0078-0456-35

300 mg Film-Coated Tablets: yellow, ovaloid, slightly biconvex, scored on both sides. Imprinted with “TE/TE” on one side and “CG/CG” on the other side.

Bottle of 100……………………………………………………………………………………………...NDC 0078-0337-05

Unit Dose (blister pack)

Box of 100 (strips of 10)…………………………………………………………………………………NDC 0078-0337-06

600 mg Film-Coated Tablets: light pink, ovaloid, slightly biconvex, scored on both sides. Imprinted with “TF/TF” on one side and “CG/CG” on the other side.

Bottle of 100……………………………………………………………………………………………...NDC 0078-0457-05

Unit Dose (blister pack)

Box of 100 (strips of 10)…………………………………………………………………………………NDC 0078-0457-35

Store at 20°C to 25°C (68°F to 77°F), excursions permitted between 15°C and 30°C (59°F and 86°F) [see USP Controlled Room Temperature]. Dispense in tight container (USP).

Suspension

300 mg/5 mL (60 mg/mL) Oral Suspension: off-white to slightly brown or slightly red suspension. Available in amber glass bottles containing 250 mL of oral suspension. Supplied with a 10 mL dosing syringe and press-in bottle adapter.

Bottle containing 250 mL of oral suspension……………………………………………………………NDC 0078-0357-52

Store TRILEPTAL oral suspension in the original container. Shake well before using.

Use within 7 weeks of first opening the bottle.

Store at 20°C to 25°C (68°F to 77°F), excursions permitted between 15°C and 30°C (59°F and 86°F) [see USP Controlled Room Temperature].

17 PATIENT COUNSELING INFORMATION

Advise the patient to read the FDA-approved patient labeling (Medication Guide and Instructions for Use).

Administration Information

Counsel patients that TRILEPTAL may be taken with or without food.

For TRILEPTAL oral suspension, advise patients to shake the bottle well and prepare the dose immediately afterwards using the oral dosing syringe supplied. Inform patients that TRILEPTAL oral suspension can be mixed in a small glass of water just prior to administration or, alternatively, may be swallowed directly from the syringe. Instruct patients to discard any unused TRILEPTAL oral suspension after 7 weeks of first opening the bottle [see Dosage and Administration (2.8) and How Supplied/Storage and Handling (16)].

Hyponatremia

Advise patients that TRILEPTAL may reduce the serum sodium concentrations especially if they are taking other medications that can lower sodium. Instruct patients to report symptoms of low sodium like nausea, tiredness, lack of energy, confusion, and more frequent or more severe seizures [see Warnings and Precautions (5.1)].

Anaphylactic Reactions and Angioedema

Anaphylactic reactions and angioedema may occur during treatment with TRILEPTAL. Advise patients to report immediately signs and symptoms suggesting angioedema (swelling of the face, eyes, lips, tongue, or difficulty in swallowing or breathing) and to stop taking the drug until they have consulted with their physician [see Warnings and Precautions (5.2)].

Cross Hypersensitivity Reaction to Carbamazepine

Inform patients who have exhibited hypersensitivity reactions to carbamazepine that approximately 25% to 30% of these patients may experience hypersensitivity reactions with TRILEPTAL. Patients should be advised that if they experience a hypersensitivity reaction while taking TRILEPTAL they should consult with their physician immediately [see Warnings and Precautions (5.3)].

Serious Dermatological Reactions

Advise patients that serious skin reactions have been reported in association with TRILEPTAL. In the event a skin reaction should occur while taking TRILEPTAL, patients should consult with their physician immediately [see Warnings and Precautions (5.4)].

Suicidal Behavior and Ideation

Patients, their caregivers, and families should be counseled that AEDs, including TRILEPTAL, may increase the risk of suicidal thoughts and behavior and should be advised of the need to be alert for the emergence or worsening of symptoms of depression, any unusual changes in mood or behavior, or the emergence of suicidal thoughts, behavior, or thoughts about self-harm. Behaviors of concern should be reported immediately to healthcare providers [see Warnings and Precautions (5.5)].

Driving and Operating Machinery

Advise patients that TRILEPTAL may cause adverse reactions, such as dizziness, somnolence, ataxia, visual disturbances, and depressed level of consciousness. Accordingly, advise patients not to drive or operate machinery until they have gained sufficient experience on TRILEPTAL to gauge whether it adversely affects their ability to drive or operate machinery [see Warnings and Precautions (5.7) and Adverse Reactions (6)].

Multi-Organ Hypersensitivity

Instruct patients that a fever associated with other organ system involvement (e.g., rash, lymphadenopathy, hepatic dysfunction) may be drug-related and should be reported to their healthcare provider immediately [see Warnings and Precautions (5.8)].

Hematologic Events

Advise patients that there have been rare reports of blood disorders reported in patients treated with TRILEPTAL. Instruct patients to immediately consult with their physician if they experience symptoms suggestive of blood disorders [see Warnings and Precautions (5.9)].

Drug Interactions

Caution female patients of reproductive potential that the concurrent use of TRILEPTAL with hormonal contraceptives may render this method of contraception less effective [see Drug Interactions (7.2) and Use in Specific Populations (8.1)]. Additional non-hormonal forms of contraception are recommended when using TRILEPTAL.

Caution should be exercised if alcohol is taken in combination with TRILEPTAL, due to a possible additive sedative effect.

Pregnancy Registry

Encourage patients to enroll in the North American Antiepileptic Drug (NAAED) Pregnancy Registry if they become pregnant. This registry is collecting information about the safety of AEDs during pregnancy [see Use in Specific Populations (8.1)].

T2025-61

MEDICATION GUIDE
TRILEPTAL (try-LĔP-tăl)
(oxcarbazepine)
film-coated tablets, for oral use
and
oral suspension

What is the most important information I should know about TRILEPTAL?
Do not stop taking TRILEPTAL without first talking to your healthcare provider. Stopping TRILEPTAL suddenly can cause serious problems.
TRILEPTAL can cause serious side effects, including:
1. TRILEPTAL may cause the level of sodium in your blood to be low. Symptoms of low blood sodium include:

• nausea

• confusion

• tiredness (lack of energy)

• more frequent or more severe seizures

• headache

Similar symptoms that are not related to low sodium may occur from taking TRILEPTAL. You should tell your healthcare provider if you have any of these side effects and if they bother you or they do not go away.
Some other medicines can also cause low sodium in your blood. Be sure to tell your healthcare provider about all the other medicines that you are taking.
Your healthcare provider may do blood tests to check your sodium levels during your treatment with TRILEPTAL.
2. TRILEPTAL may also cause allergic reactions or serious problems which may affect organs and other parts of your body like the liver or blood cells. You may or may not have a rash with these types of reactions.
Call your healthcare provider right away if you have any of the following:

• swelling of your face, eyes, lips, or tongue

• painful sores in the mouth or around your eyes

• trouble swallowing or breathing

• yellowing of your skin or eyes

• a skin rash

• unusual brusing or bleeding

• hives

• severe fatigue or weakness

• fever, swollen glands, or sore throat that do not go away or come and go

• severe muscle pain

• frequent infections or infections that do not go away

Many people who are allergic to carbamazepine are also allergic to TRILEPTAL. Tell your healthcare provider if you are allergic to carbamazepine.
3. Like other antiepileptic drugs (AEDs), TRILEPTAL may cause suicidal thoughts or actions in a very small number of people, about 1 in 500.
Call a healthcare provider right away if you have any of these symptoms, especially if they are new, worse, or worry you:

• thoughts about suicide or dying

• trouble sleeping (insomnia)

• attempts to commit suicide

• new or worse irritability

• new or worse depression

• acting aggressive, being angry, or violent

• new or worse anxiety

• acting on dangerous impulses

• feeling agitated or restless

• an extreme increase in activity and talking (mania)

• panic attacks

• other unusual changes in behavior or mood

How can I watch for early symptoms of suicidal thoughts and actions?

- Pay attention to any changes, especially sudden changes, in mood, behaviors, thoughts, or feelings.
- Keep all follow-up visits with your healthcare provider as scheduled.

Call your healthcare provider between visits as needed, especially if you are worried about symptoms.
Do not stop taking TRILEPTAL without first talking to a healthcare provider.

- Stopping TRILEPTAL suddenly can cause serious problems.
- Stopping a seizure medicine suddenly in a patient who has epilepsy may cause seizures that will not stop (status epilepticus).

Suicidal thoughts or actions may be caused by things other than medicines. If you have suicidal thoughts or actions, your healthcare provider may check for other causes.

What is TRILEPTAL?
TRILEPTAL is a prescription medicine used:

- alone or with other medicines to treat partial-onset seizures in adults
- alone to treat partial-onset seizures in children 4 years of age and older
- with other medicines to treat partial-onset seizures in children 2 years of age and older

It is not known if TRILEPTAL is safe and effective for use alone to treat partial-onset seizures in children less than 4 years of age or for use with other medicines to treat partial-onset seizures in children less than 2 years of age.

Do not take TRILEPTAL if you are allergic to TRILEPTAL or any of the other ingredients in TRILEPTAL, or to eslicarbazepine acetate. See the end of this Medication Guide for a complete list of ingredients in TRILEPTAL.
Many people who are allergic to carbamazepine are also allergic to TRILEPTAL. Tell your healthcare provider if you are allergic to carbamazepine.

Before taking TRILEPTAL, tell your healthcare provider about all your medical conditions, including if you:

- have or have had suicidal thoughts or actions, depression or mood problems
- have liver problems
- have kidney problems
- are allergic to carbamazepine. Many people who are allergic to carbamazepine are also allergic to TRILEPTAL.
- use birth control medicine. TRILEPTAL may cause your birth control medicine to be less effective. Talk to your healthcare provider about the best birth control method to use.
- are pregnant or plan to become pregnant. It is not known if TRILEPTAL may harm your unborn baby. Tell your healthcare provider right away if you become pregnant while taking TRILEPTAL. You and your healthcare provider will decide if you should take TRILEPTAL while you are pregnant.
  If you become pregnant while taking TRILEPTAL, talk to your healthcare provider about registering with the North American Antiepileptic Drug (NAAED) Pregnancy Registry. The purpose of this registry is to collect information about the safety of antiepileptic medicine during pregnancy. You can enroll in this registry by calling 1-888-233-2334.
- are breastfeeding or plan to breastfeed. TRILEPTAL passes into breast milk. Talk with your healthcare provider about the best way to feed your baby if you take TRILEPTAL.

Tell your healthcare provider about all the medicines you take, including prescription and over-the-counter medicines, vitamins, and herbal supplements. Taking TRILEPTAL with certain other medicines may cause side effects or affect how well they work. Do not start or stop other medicines without talking to your healthcare provider.
Know the medicines you take. Keep a list of them to show your healthcare provider and pharmacist when you get a new medicine.

How should I take TRILEPTAL?

- Do not stop taking TRILEPTAL without talking to your healthcare provider. Stopping TRILEPTAL suddenly can cause serious problems, including seizures that will not stop (status epilepticus).
- Take TRILEPTAL exactly as prescribed. Your healthcare provider may change your dose. Your healthcare provider will tell you how much TRILEPTAL to take.
- Take TRILEPTAL 2 times a day.
- Take TRILEPTAL with or without food.
- Before taking TRILEPTAL oral suspension shake the bottle well and use the oral dosing syringe that comes with your oral suspension to measure the amount of medicine needed. TRILEPTAL oral suspension can be mixed in a small glass of water, or swallowed directly from the syringe. Clean the syringe with warm water and let it dry after each use.
- If you take too much TRILEPTAL, call your healthcare provider right away.

What should I avoid while taking TRILEPTAL?

- Do not drive or operate machinery until you know how TRILEPTAL affects you. TRILEPTAL may slow your thinking and motor skills.
- Do not drink alcohol or take other drugs that make you sleepy or dizzy while taking TRILEPTAL until you talk to your healthcare provider. TRILEPTAL taken with alcohol or drugs that cause sleepiness or dizziness may make your sleepiness or dizziness worse.

What are the possible side effects of TRILEPTAL?
See “What is the most important information I should know about TRILEPTAL?”
TRILEPTAL may cause other serious side effects, including:

- trouble concentrating
- problems with your speech and language
- feeling confused
- feeling sleepy and tired
- trouble with walking and coordination
- seizures that can happen more often or become worse, especially in children

Get medical help right away if you have any of the symptoms listed above or listed in “What is the most important information I should know about TRILEPTAL?”
The most common side effects of TRILEPTAL include:

• dizziness

• problems with vision

• sleepiness

• trembling

• double vision

• problems with walking and coordination (unsteadiness)

• tiredness

• rash

• nausea

• headache

• vomiting

These are not all the possible side effects of TRILEPTAL. Tell your healthcare provider if you have any side effect that bothers you or does not go away.
Call your doctor for medical advice about side effects. You may report side effects to FDA at 1-800-FDA-1088.

How should I store TRILEPTAL?

- Store TRILEPTAL film-coated tablets and oral suspension at room temperature between 68°F to 77°F (20°C to 25°C) . Keep TRILEPTAL film-coated tablets dry.
- Keep TRILEPTAL oral suspension in the original container and use within 7 weeks of first opening the bottle. Shake well before each use.

Keep TRILEPTAL and all medicines out of the reach of children.

General Information about the safe and effective use of TRILEPTAL.
Medicines are sometimes prescribed for purposes other than those listed in a Medication Guide. Do not use TRILEPTAL for a condition for which it was not prescribed. Do not give TRILEPTAL to other people, even if they have the same symptoms that you have. It may harm them.
You can ask your pharmacist or healthcare provider for information about TRILEPTAL that is written for health professionals.

What are the ingredients in TRILEPTAL?
Active ingredient: oxcarbazepine
Inactive ingredients:

- Film-coated tablets: colloidal silicon dioxide, crospovidone, hydroxypropyl methylcellulose, iron oxide, magnesium stearate, microcrystalline cellulose, polyethylene glycol, talc and titanium dioxide.
- Oral suspension: ascorbic acid, dispersible cellulose, ethanol, macrogol stearate, methyl parahydroxybenzoate, propylene glycol, propyl parahydroxybenzoate, purified water, sodium saccharin, sorbic acid, sorbitol, yellow-plum-lemon aroma.

Distributed by: Novartis Pharmaceuticals Corporation, East Hanover, New Jersey 07936
© Novartis
For more information, go to www.novartis.us or call 1-888-669-6682.

This Medication Guide has been approved by the U.S. Food and Drug Administration

Revised: 9/2025

T2025-62

INSTRUCTIONS FOR USE
TRILEPTAL® [try-LĔP-tăl]
(oxcarbazepine)
oral suspension

This Instructions for Use contains information on how to take or give TRILEPTAL. Read this Instructions for Use before you take or give TRILEPTAL oral suspension and each time you get a refill. There may be new information. This information does not take the place of talking to your healthcare provider about your medical condition or treatment.

Important Information You Need to Know Before Taking or Giving TRILEPTAL Oral Suspension

- Follow the healthcare provider’s instructions for how to take or give TRILEPTAL oral suspension. Do not stop taking TRILEPTAL oral suspension without first talking to a healthcare provider.
- Always use the oral dosing syringe provided to make sure you measure the right amount of TRILEPTAL oral suspension. If you need a new dosing syringe contact your pharmacist. Do not use a household teaspoon or tablespoon.
- Shake the closed bottle of oral suspension well before each use.
- Use TRILEPTAL oral suspension within 7 weeks of first opening the bottle. Throw away (dispose of) the bottle and syringe when you have finished the oral suspension or 7 weeks after opening the bottle.
- Call your healthcare provider or pharmacist if you have any questions about how to prepare and take or give TRILEPTAL oral suspension the right way.
- If you take or give too much TRILEPTAL, call the healthcare provider right away.

The TRILEPTAL pack contains a bottle of TRILEPTAL oral suspension, press-in bottle adaptor, and oral dosing syringe. These 3 supplies are needed to prepare and take or give TRILEPTAL oral suspension.

1. Plastic bottle adapter that you push into the neck of the bottle the first time you open the bottle.
Do not remove adapter after it is inserted.

2. Bottle containing 250 mL of TRILEPTAL oral suspension, with a child-resistant cap. Always replace the cap after each use.

3. 10 mL oral dosing syringe that fits into the plastic bottle adapter to withdraw the prescribed dose of medicine from the bottle.

Section A: Preparing the TRILEPTAL Oral Suspension Bottle

Step 1. Shake the bottle of medicine for at least 10 seconds.
Step 2. Remove the child-resistant cap by pushing it down firmly and turning it to the left (counterclockwise, as shown on the top of the cap).
Note: Save the cap so you can close the bottle after each use.

Step 3. Hold the open bottle upright on a table and push the plastic adapter firmly into the neck of the bottle as far as possible.
Step 4. Replace the cap to be sure that the adapter has been fully forced into the neck of the bottle.
Note: You may not be able to push the adapter fully down, but it will be forced into the bottle when you screw the cap back on.
The bottle is now ready to be used with the syringe.
The adapter must always stay in the bottle. The child-resistant cap should seal the bottle in between use.

Section B: Prepare the Dose of TRILEPTAL Oral Suspension

Step 5. Shake the bottle well. Prepare the dose right away.
Step 6. Push and turn the child-resistant cap to open the bottle.
Note: Always replace the cap after use.

Step 7. Check that the plunger is all the way down inside the barrel of the syringe before inserting the syringe into the bottle.
Step 8. Keep the bottle upright and push the syringe firmly into the plastic adapter.

Step 9. Hold the syringe in place and carefully turn the bottle upside down.
Step 10. Slowly pull the plunger out so that the syringe fills with some medicine. Push the plunger back in just far enough to completely push out any large air bubbles that may be trapped in the syringe.
Then pull down on the plunger again and keep doing this until there are no air bubbles present. Small air bubbles are okay.

Step 11. Slowly pull the plunger out until the top edge of the plunger is exactly level with the marker on the syringe barrel for the prescribed dose.
Note: If the prescribed dose is more than 10 mL, you will need to refill the syringe to make up the full dose.

Step 12. Carefully turn the bottle upright. Take out the syringe by gently twisting it out of the plastic adapter.
The plastic adapter should stay in the bottle.

Section C: Take or Give TRILEPTAL Oral Suspension

Step 13. You can mix the dose of medicine in a small glass of water before it is swallowed, or you can swallow it or give it directly from the syringe.
a. If you mix the medicine with water, add some water to a glass. Push in the plunger on the syringe all the way to empty all the medicine into the glass. Stir the medicine in the water and drink or give it all.
b. If you use the syringe to take or give the medicine, the person must sit upright. Push the plunger slowly to let the person swallow the medicine.
Step 14. Screw the child-resistant cap back on the bottle tightly, by turning the cap to the right (clockwise).
Step 15. Clean the syringe after use. Rinse the syringe with warm water and allow it to dry thoroughly.

Section D: Storing TRILEPTAL Oral Suspension

- Store TRILEPTAL oral suspension at room temperature between 68°F to 77°F (20°C to 25°C) in the original bottle.
- Shake the bottle well before each use.
- Keep TRILEPTAL oral suspension in the original container and use within 7 weeks of first opening the bottle. Throw away (dispose of) the syringe and bottle when you have finished the oral suspension or 7 weeks after first opening.
- Keep TRILEPTAL and all medicines out of the reach of children.

Distributed by:
Novartis Pharmaceuticals Corporation
East Hanover, New Jersey 07936
© Novartis

This Instructions for Use has been approved by the U.S. Food and Drug Administration.

Revised: 9/2025

T2025-63

PRINCIPAL DISPLAY PANEL

NDC 0078-0456-05

Trileptal® 150 mg
(oxcarbazepine)

100 tablets

Rx only

PHARMACIST: DISPENSE WITH
MEDICATION GUIDE ATTACHED
OR PROVIDED SEPARATELY.

NOVARTIS

PRINCIPAL DISPLAY PANEL

NDC 0078-0337-05

Trileptal® 300 mg
(oxcarbazepine)

100 tablets

Rx only

PHARMACIST: DISPENSE WITH
MEDICATION GUIDE ATTACHED
OR PROVIDED SEPARATELY.

NOVARTIS

PRINCIPAL DISPLAY PANEL

NDC 0078-0457-05

Trileptal® 600 mg
(oxcarbazepine)

100 tablets

Rx only

PHARMACIST: DISPENSE
WITH MEDICATION GUIDE
ATTACHED OR PROVIDED
SEPARATELY.

NOVARTIS

PRINCIPAL DISPLAY PANEL

NDC 0078-0357-52

Rx only

Trileptal®
(oxcarbazepine)

Oral Suspension

300 mg/5 mL

PHARMACIST: DISPENSE WITH
MEDICATION GUIDE ENCLOSED
OR PROVIDED SEPARATELY

Shake well before using.

Each 5 mL contains 300 mg oxcarbazepine.

250 mL

NOVARTIS